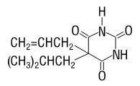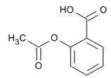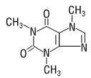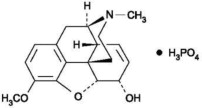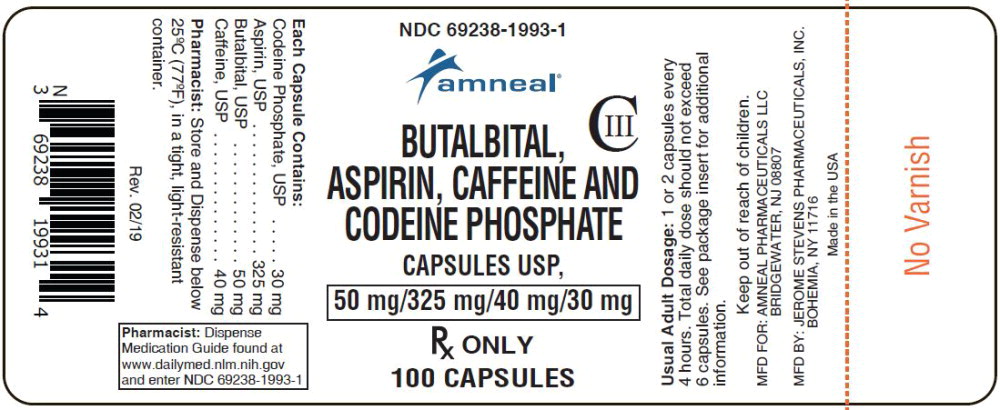 DRUG LABEL: BUTALBITAL, ASPIRIN, CAFFEINE and CODEINE PHOSPHATE
NDC: 69238-1993 | Form: CAPSULE
Manufacturer: Amneal Pharmaceuticals of New York, LLC
Category: prescription | Type: HUMAN PRESCRIPTION DRUG LABEL
Date: 20260115
DEA Schedule: CIII

ACTIVE INGREDIENTS: BUTALBITAL 50 mg/1 1; ASPIRIN 325 mg/1 1; CAFFEINE 40 mg/1 1; CODEINE PHOSPHATE 30 mg/1 1
INACTIVE INGREDIENTS: D&C YELLOW NO. 10; ALUMINUM OXIDE; D&C RED NO. 33; D&C RED NO. 28; FD&C BLUE NO. 1; FD&C BLUE NO. 2; FD&C RED NO. 40; GELATIN; CELLULOSE, MICROCRYSTALLINE; STARCH, CORN; TALC; TITANIUM DIOXIDE; STEARIC ACID; SILICON DIOXIDE

HIGHLIGHTS OF PRESCRIBING INFORMATION

These highlights do not include all the information needed to use BUTALBITAL, ASPIRIN, CAFFEINE and CODEINE PHOSPHATE capsules safely and effectively. See full prescribing information for BUTALBITAL, ASPIRIN, CAFFEINE and CODEINE PHOSPHATE.
BUTALBITAL, ASPIRIN, CAFFEINE and CODEINE PHOSPHATE capsules, USP, for oral use Initial U.S. Approval: 1990

RECENT MAJOR CHANGES

Boxed Warning | 11/2025
Indications and Usage (1) | 11/2025
Dosage and Administration (2.2, 2.4) | 11/2025
Warning and Precautions (5.1, 5.2, 5.3, 5.14, 5.16) | 11/2025

WARNING: SERIOUS AND LIFE-THREATENING RISKS FROM USE OF BUTALBITAL, ASPIRIN, CAFFEINE and CODEINE PHOSPHATE.

See full prescribing information for complete boxed warning.

- BUTALBITAL, ASPIRIN, CAFFEINE and CODEINE PHOSPHATE exposes users to the risks of addiction, abuse, and misuse, which can lead to overdose and death. Assess patient's risk before prescribing and monitor regularly for these behaviors and conditions. (5.1)
- Serious, life-threatening, or fatal respiratory depression may occur. Monitor closely, especially upon initiation or following a dose increase. (5.2)
- Accidental ingestion of BUTALBITAL, ASPIRIN, CAFFEINE and CODEINE PHOSPHATE, especially by children, can result in fatal overdose. (5.2)
- Concomitant use of opioids or a barbiturate with benzodiazepines or other central nervous system (CNS) depressants, including alcohol, may result in profound sedation, respiratory depression, coma, and death. Reserve concomitant prescribing for use in patients for whom alternative treatment options are inadequate; limit dosages and durations to the minimum required; and follow patients for signs and symptoms of respiratory depression and sedation. (5.3, 5.9, 7)
- Advise pregnant women using opioids for an extended period of time of the risk of Neonatal Opioid Withdrawal Syndrome, which may be life-threatening if not recognized and treated. Ensure that management by neonatology experts will be available at delivery. (5.4)
- To ensure that the benefits of opioid analgesics outweigh the risks of addiction, abuse and misuse, the Food and Drug Administration (FDA) has required a Risk Evaluation and Mitigation Strategy (REMS) for these products (5.5)
- Life-threatening respiratory depression and death have occurred in children who received codeine; most cases followed tonsillectomy and/or adenoidectomy, and many of the children had evidence of being an ultra-rapid metabolizer of codeine due to a CYP2D6 polymorphism. (5.6) BUTALBITAL, ASPIRIN, CAFFEINE and CODEINE PHOSPHATE is contraindicated in children younger than 12 years of age and in children younger than 18 years of age following tonsillectomy and/or adenoidectomy (4). Avoid the use of BUTALBITAL, ASPIRIN, CAFFEINE and CODEINE PHOSPHATE in adolescents 12 to 18 years of age who have other risk factors that may increase their sensitivity to the respiratory depressant effects of codeine.
- The effects of concomitant use or discontinuation of cytochrome P450 3A4 inducers, 3A4 inhibitors, or 2D6 inhibitors with codeine are complex. Use of cytochrome P450 3A4 inducers, 3A4 inhibitors, or 2D6 inhibitors with BUTALBITAL, ASPIRIN, CAFFEINE and CODEINE PHOSPHATE requires careful consideration of the effects on codeine, and the active metabolite, morphine. (5.7, 5.9, 7)

1 INDICATIONS AND USAGE

BUTALBITAL, ASPIRIN, CAFFEINE and CODEINE PHOSPHATE is a combination of butalbital, a barbiturate, aspirin, a nonsteroidal anti-inflammatory drug, caffeine, a methylxanthine, and codeine phosphate, an opioid agonist, and is indicated for the management of the symptom complex of tension (or muscle contraction) headache, when other non-opioid analgesics and alternative treatments are inadequate.

Limitations of Use

Because of the risks of addiction, abuse, misuse, overdose, and death, which can occur at any dosage or duration and persist over the course of therapy, reserve opioid analgesics, including BUTALBITAL, ASPIRIN, CAFFEINE and CODEINE PHOSPHATE for use in patients for whom alternative treatment options are ineffective, not tolerated, or would be otherwise inadequate to provide sufficient management of pain (1, 5.1).

BUTALBITAL, ASPIRIN, CAFFEINE and CODEINE PHOSPHATE should not be used for an extended period of time unless the pain remains severe enough to require an opioid analgesic and for which alternative treatment options continue to be inadequate.

2 DOSAGE AND ADMINISTRATION

- Periodically reassess patients receiving BUTALBITAL, ASPIRIN, CAFFEINE and CODEINE PHOSPHATE to evaluate the continued need for opioid analgesics to maintain pain control, for the signs or symptoms of adverse reactions, and for the development of addiction, abuse, or misuse.
- Use the lowest effective dosage for the shortest duration of time consistent with individual patient treatment goals. Reserve titration to higher doses of BUTALBITAL, ASPIRIN, CAFFEINE and CODEINE PHOSPHATE for patients in whom lower doses are insufficiently effective and in whom the expected benefits of using a higher dose opioid clearly outweigh the substantial risks. (2.1, 5)
- Initiate the dosing regimen for each patient individually, taking into account the patient's underlying cause and severity of pain, prior analgesic treatment and response, and risk factors for addiction, abuse, and misuse (2.1, 5.1)
- Discuss availability of naloxone with the patient and caregiver and assess each patient's need for access to naloxone, both when initiating and renewing treatment with BUTALBITAL, ASPIRIN, CAFFEINE and CODEINE PHOSPHATE. Consider prescribing naloxone based on the patient's risk factors for overdose. (2.2, 5.1, 5.2, 5.3)
- Discuss opioid overdose reversal agents and options for acquiring them with the patient and/or caregiver, both when initiating and renewing treatment with BUTALBITAL, ASPIRIN, CAFFEINE and CODEINE PHOSPHATE, especially if the patient has additional risk factors for overdose, or close contacts at risk for exposure and overdose. (2.2, 5.1, 5.2, 5.3)
- BUTALBITAL, ASPIRIN, CAFFEINE and CODEINE PHOSPHATE should be prescribed only by healthcare professionals who are knowledgeable about the use of opioids and how to mitigate the associated risks. (2.1)
- Many acute pain conditions (e.g., the pain that occurs with a number of surgical procedures or acute musculoskeletal injuries) require no more than a few days of an opioid analgesic. Clinical guidelines on opioid prescribing for some acute pain conditions are available. (2.1)
- Respiratory depression can occur at any time during opioid therapy, especially when initiating and following dosage increases with BUTALBITAL, ASPIRIN, CAFFEINE and CODEINE PHOSPHATE. Consider this risk when selecting an initial dose and when making dose adjustments. (2.1, 5.2)
- Initiate treatment with one or two capsules every 4 hours as needed for pain and at the lowest dose necessary to achieve adequate analgesia. Titrate the dose based upon the individual patient's response to their initial dose of BUTALBITAL, ASPIRIN, CAFFEINE and CODEINE PHOSPHATE. Total daily dosage should not exceed 6 capsules. (2, 5)
- Do not rapidly reduce or abruptly discontinue BUTALBITAL, ASPIRIN, CAFFEINE and CODEINE PHOSPHATE in a physically dependent patient because rapid reduction or abrupt discontinuation of opioid analgesics has resulted in serious withdrawal symptoms, uncontrolled pain, and suicide. (2.4, 5.16)

3 DOSAGE FORMS AND STRENGTHS

Capsules: 50 mg butalbital, 325 mg aspirin, 40 mg caffeine, and 30 mg codeine phosphate (3)

4 CONTRAINDICATIONS

- Children younger than 12 years of age (4)
- Post-operative management in children younger than 18 years of age following tonsillectomy and/or adenoidectomy (4)
- Significant respiratory depression (4)
- Acute or severe bronchial asthma (4)
- Concurrent use of monoamine oxidase inhibitors (MAOIs) or use of MAOIs within the last 14 days (4)
- Known or suspected gastrointestinal obstruction, including paralytic ileus (4)
- Hypersensitivity to aspirin, caffeine, butalbital, or codeine (4)
- Hemophilia (4)
- Reye's Syndrome (4)
- Known allergy to NSAIDs (4)
- Syndrome of asthma, rhinitis, and nasal polyps (4)

5 WARNINGS AND PRECAUTIONS

- Opioid-Induced Hyperalgesia and Allodynia: Opioid-Induced Hyperalgesia (OIH) occurs when an opioid analgesic paradoxically causes an increase in pain, or an increase in sensitivity to pain. If OIH is suspected, carefully consider appropriately decreasing the dose of the current opioid analgesic, or opioid rotation. (5.8)
- Life-Threatening Respiratory Depression in Patients with Chronic Pulmonary Disease or in Elderly, Cachectic, or Debilitated Patients: Regularly evaluate, particularly during initiation and titration. (5.9)
- Adrenal Insufficiency: If diagnosed, treat with physiologic replacement of corticosteroids, and wean patient off the opioid. (5.11)
- Severe Hypotension: Regularly evaluate during dose initiation and titration. Avoid use of BUTALBITAL, ASPIRIN, CAFFEINE and CODEINE PHOSPHATE in patients with circulatory shock. (5.12)
- Risks of Use in Patients with Increased Intracranial Pressure, Brain Tumors, Head Injury, or Impaired Consciousness: Regularly evaluate for sedation and respiratory depression. Avoid use of BUTALBITAL, ASPIRIN, CAFFEINE and CODEINE PHOSPHATE in patients with impaired consciousness or coma. (5.13)
- Fetal toxicity: Limit use of NSAIDs, including BUTALBITAL, ASPIRIN, CAFFEINE and CODEINE PHOSPHATE, between about 20 to 30 weeks in pregnancy due to the risk of oligohydramnios/fetal renal dysfunction. Avoid use of NSAIDs in women at about 30 weeks gestation and later in pregnancy due to the risks of oligohydramnios/fetal renal dysfunction and premature closure of the fetal ductus arteriosus. (5.17, 8.1)
- Drug Reaction with Eosinophilia and Systemic Symptoms (DRESS): Discontinue and evaluate clinically. (5.21)

6 ADVERSE REACTIONS

Most common adverse reactions (incidence > 1%) are nausea and/or abdominal pain, drowsiness, and dizziness. (6)

To report SUSPECTED ADVERSE REACTIONS, contact Amneal Pharmaceuticals at 1-877-835-5472 or FDA at 1-800-FDA-1088 or www.fda.gov/medwatch.

7 DRUG INTERACTIONS

- Serotonergic Drugs: Concomitant use may result in serotonin syndrome. Discontinue BUTALBITAL, ASPIRIN, CAFFEINE and CODEINE PHOSPHATE if serotonin syndrome is suspected. (7)
- Mixed Agonist/Antagonist and Partial Agonist Opioid Analgesics: Avoid use with BUTALBITAL, ASPIRIN, CAFFEINE and CODEINE PHOSPHATE because they may reduce analgesic effect of BUTALBITAL, ASPIRIN, CAFFEINE and CODEINE PHOSPHATE or precipitate withdrawal symptoms. (7)

8 USE IN SPECIFIC POPULATIONS

- Pregnancy: May cause fetal harm (8.1)
- Lactation: Breastfeeding not recommended. (8.2)

Pharmacist: Dispense Medication Guide found at www.dailymed.nlm.nih.gov and enter NDC 69238-1993-1

FULL PRESCRIBING INFORMATION

WARNING: SERIOUS AND LIFE-THREATENING RISKS FROM USE OF BUTALBITAL, ASPIRIN, CAFFEINE and CODEINE PHOSPHATE.

Addiction, Abuse, and Misuse

Because the use of BUTALBITAL, ASPIRIN, CAFFEINE and CODEINE PHOSPHATE exposes patients and other users to the risks of opioid addiction, abuse, and misuse, which can lead to overdose and death, assess each patient's risk prior to prescribing and reassess all patients regularly for the development of these behaviors and conditions

[see Warnings and Precautions (5.1)].

Life-Threatening Respiratory Depression

Serious, life-threatening, or fatal respiratory depression may occur with use of BUTALBITAL, ASPIRIN, CAFFEINE and CODEINE PHOSPHATE, especially during initiation or following a dosage increase. To reduce the risk of respiratory depression, proper dosing and titration of BUTALBITAL, ASPIRIN, CAFFEINE and CODEINE PHOSPHATE are essential [see Warnings and Precautions (5.2)]

Accidental Ingestion

Accidental ingestion of even one dose of BUTALBITAL, ASPIRIN, CAFFEINE and CODEINE PHOSPHATE, especially by children, can result in a fatal overdose of aspirin, butalbital, caffeine and codeine phosphate [see Warnings and Precautions (5.2)].

Risks From Concomitant Use With Benzodiazepines Or Other CNS Depressants

Concomitant use of opioids with benzodiazepines or other central nervous system (CNS) depressants, including alcohol, may result in profound sedation, respiratory depression, coma, and death. Reserve concomitant prescribing of BUTALBITAL, ASPIRIN, CAFFEINE and CODEINE PHOSPHATE and benzodiazepines or other CNS depressants for use in patients for whom alternative treatment options are inadequate. [see Warnings and Precautions (5.3, 5.9), Drug Interactions (7)].

Neonatal Opioid Withdrawal Syndrome (NOWS)

Advise pregnant women using opioids for an extended period of time of the risk of Neonatal Opioid Withdrawal Syndrome, which may be life-threatening if not recognized and treated. Ensure that management by neonatology experts will be available at delivery [see Warnings and Precautions (5.4)].

Opioid Analgesic Risk Evaluation and Mitigation Strategy (REMS)

Healthcare providers are strongly encouraged to complete a REMScompliant education program and to counsel patients and caregivers on serious risks, safe use, and the importance of reading the Medication Guide with each prescription [see Warnings and Precautions (5.5)].

Ultra-Rapid Metabolism of Codeine and Other Risk Factors for Life-Threatening Respiratory Depression in Children

Life-threatening respiratory depression and death have occurred in children who received codeine. Most of the reported cases occurred following tonsillectomy and/or adenoidectomy, and many of the children had evidence of being an ultra-rapid metabolizer of codeine due to a CYP2D6 polymorphism. [see Warnings and Precautions (5.6)]. BUTALBITAL, ASPIRIN, CAFFEINE and CODEINE PHOSPHATE is contraindicated in children younger than 12 years of age and in children younger than 18 years of age following tonsillectomy and/or adenoidectomy [see Contraindications (4)]. Avoid the use of BUTALBITAL, ASPIRIN, CAFFEINE and CODEINE PHOSPHATE in adolescents 12 to 18 years of age who have other risk factors that may increase their sensitivity to the respiratory depressant effects of codeine.

Interactions with Drugs Affecting Cytochrome P450 Isoenzymes

The effects of concomitant use or discontinuation of cytochrome P450 3A4 inducers, 3A4 inhibitors, or 2D6 inhibitors with codeine are complex. Use of cytochrome P450 3A4 inducers, 3A4 inhibitors, or 2D6 inhibitors with BUTALBITAL, ASPIRIN, CAFFEINE and CODEINE PHOSPHATE requires careful consideration of the effects on codeine, and the active metabolite, morphine [see Warnings and Precautions (5.7, 5.9), Drug Interactions (7)].

1 INDICATIONS AND USAGE

BUTALBITAL, ASPIRIN, CAFFEINE and CODEINE PHOSPHATE is indicated for the management of the symptom complex of tension (or muscle contraction) headache, when non-opioid analgesic and alternative treatments are inadequate.

Limitations of Use

Because of the risks of addiction, abuse, misuse, overdose, and death, which can occur at any dosage or duration and persist over the course of therapy [see Warnings and Precautions (5.1)] , reserve opioid analgesics, including BUTALBITAL, ASPIRIN, CAFFEINE and CODEINE PHOSPHATE for use in patients for whom alternative treatment options are ineffective, not tolerated, or would be otherwise inadequate to provide sufficient management of pain.

BUTALBITAL, ASPIRIN, CAFFEINE and CODEINE PHOSPHATE should not be used for an extended period of time unless the pain remains severe enough to require an opioid analgesic and for which alternative treatment options continue to be inadequate.

2 DOSAGE AND ADMINISTRATION

2.1 Important Dosage and Administration Instructions

- Use the lowest effective dosage for the shortest duration of time consistent with individual patient treatment goals [see Warnings and Precautions (5)]. Because the risk of overdose increases as opioid doses increase, reserve titration to higher doses of BUTALBITAL, ASPIRIN, CAFFEINE and CODEINE PHOSPHATE for patients in whom lower doses are insufficiently effective and in whom the expected benefits of using a higher dose opioid clearly outweigh the substantial risks.
- There is variability in the opioid analgesic dose and duration needed to adequately manage pain due both to the cause of pain and to individual patient factors. Initiate the dosing regimen for each patient individually, taking into account the patient's underlying cause and severity of pain, prior analgesic treatment and response, and risk factors for addiction, abuse, and misuse [see Warnings and Precautions (5.1)].
- BUTALBITAL, ASPIRIN, CAFFEINE and CODEINE PHOSPHATE should be prescribed only by healthcare professionals who are knowledgeable about the use of opioids and how to mitigate the associated risks.
- Many acute pain conditions (e.g., the pain that occurs with a number of surgical procedures or acute musculoskeletal injuries) require no more than a few days of an opioid analgesic. Clinical guidelines on opioid prescribing for some acute pain conditions are available.
- Respiratory depression can occur at any time during opioid therapy, especially when initiating and following dosage increases with BUTALBITAL, ASPIRIN, CAFFEINE and CODEINE PHOSPHATE. Consider this risk when selecting an initial dose and when making dose adjustments [see Warnings and Precautions (5)].

2.2 Patient Access to an Opioid Overdose Reversal Agent for the Emergency Treatment of Opioid Overdose

Inform patients and caregivers about opioid overdose reversal agents (e.g., naloxone, nalmefene). Discuss the importance of having access to an opioid overdose reversal agent, especially if the patient has risk factors for overdose (e.g., concomitant use of CNS depressants, a history of opioid use disorder, or prior opioid overdose) or if there are household members (including children) or other close contacts at risk for accidental ingestion or opioid overdose. The presence of risk factors for overdose should not prevent the management of pain in any patient [see Warnings and Precautions (5.1, 5.2, 5.3)].

Discuss the options for obtaining an opioid overdose reversal agent (e.g., prescription, over-the-counter, or as part of a community-based program) [see Warnings and Precautions (5.2)].

There are important differences among the opioid overdose reversal agents, such as route of administration, product strength, approved patient age range, and pharmacokinetics. Be familiar with these differences, as outlined in the approved labeling for those products, prior to recommending or prescribing such an agent.

2.3 Dosing Information

One or two capsules every 4 hours as needed for pain. Total daily dosage should not exceed 6 capsules. Use the lowest dose necessary to achieve adequate analgesia. Titrate the dose based upon the individual patient's response to their initial dose of BUTALBITAL, ASPIRIN, CAFFEINE and CODEINE PHOSPHATE.

2.4 Safe Reduction or Discontinuation of BUTALBITAL, ASPIRIN, CAFFEINE and CODEINE PHOSPHATE

Do not rapidly reduce or abruptly discontinue BUTALBITAL, ASPIRIN, CAFFEINE and CODEINE PHOSPHATE in patients who may be physically dependent on opioids. Rapid reduction or abrupt discontinuation of opioid analgesics in patients who are physically dependent on opioids has resulted in serious withdrawal symptoms, uncontrolled pain, and suicide. Rapid reduction or abrupt discontinuation has also been associated with attempts to find other sources of opioid analgesics, which may be confused with drug-seeking for abuse. Patients may also attempt to treat their pain or withdrawal symptoms with illicit opioids, such as heroin, and other substances.

When a decision has been made to decrease the dose or discontinue therapy in an opioid dependent patient taking BUTALBITAL, ASPIRIN, CAFFEINE and CODEINE PHOSPHATE, there are a variety of factors that should be considered, including the total daily dose of opioid (including BUTALBITAL, ASPIRIN, CAFFEINE and CODEINE PHOSPHATE) the patient has been taking, the duration of treatment, the type of pain being treated, and the physical and psychological attributes of the patient. It is important to ensure ongoing care of the patient and to agree on an appropriate tapering schedule and follow-up plan so that patient and provider goals and expectations are clear and realistic. When opioid analgesics are being discontinued due to a suspected substance use disorder, evaluate and treat the patient, or refer for evaluation and treatment of the substance use disorder. Treatment should include evidence-based approaches, such as medication assisted treatment of opioid use disorder. Complex patients with co-morbid pain and substance use disorders may benefit from referral to a specialist.

There are no standard opioid tapering schedules that are suitable for all patients. Good clinical practice dictates a patient-specific plan to taper the dose of the opioid gradually. For patients on BUTALBITAL, ASPIRIN, CAFFEINE and CODEINE PHOSPHATE who are physically opioid-dependent, initiate the taper by a small enough increment (e.g., no greater than 10% to 25% of the total daily dose) to avoid withdrawal symptoms, and proceed with dose-lowering at an interval of every 2 to 4 weeks. Patients who have been taking opioids for briefer periods of time may tolerate a more rapid taper.

It may be necessary to provide the patient with lower dosage strengths to accomplish a successful taper. Reassess the patient frequently to manage pain and withdrawal symptoms, should they emerge. Common withdrawal symptoms include restlessness, lacrimation, rhinorrhea, yawning, perspiration, chills, myalgia, and mydriasis. Other signs and symptoms also may develop, including irritability, anxiety, backache, joint pain, weakness, abdominal cramps, insomnia, nausea, anorexia, vomiting, diarrhea, or increased blood pressure, respiratory rate, or heart rate. If withdrawal symptoms arise, it may be necessary to pause the taper for a period of time or raise the dose of the opioid analgesic to the previous dose, and then proceed with a slower taper. In addition, evaluate patients for any changes in mood, emergence of suicidal thoughts, or use of other substances.

When managing patients taking opioid analgesics, particularly those who have been treated for an extended period of time, and/or with high doses for chronic pain, ensure that a multimodal approach to pain management, including mental health support (if needed), is in place prior to initiating an opioid analgesic taper. A multimodal approach to pain management may optimize the treatment of chronic pain, as well as assist with the successful tapering of the opioid analgesic [see Warnings and Precautions (5.16), Drug Abuse and Dependence (9.3)].

3 DOSAGE FORMS AND STRENGTHS

Capsules : Butalbital, 50 mg, Aspirin, 325 mg, Caffeine, 40 mg, Codeine Phosphate, 30 mg Yellow and blue Capsule imprinted with JSP 507.

4 CONTRAINDICATIONS

BUTALBITAL, ASPIRIN, CAFFEINE and CODEINE PHOSPHATE is contraindicated for:

- All children younger than 12 years of age [see Warnings and Precautions (5.6)]
- Postoperative management in children younger than 18 years of age following tonsillectomy and/or adenoidectomy[see Warnings and Precautions (5.6)].

BUTALBITAL, ASPIRIN, CAFFEINE and CODEINE PHOSPHATE is also contraindicated in patients with:

- Significant respiratory depression [see Warnings and Precautions (5.9)]
- Acute or severe bronchial asthma in an unmonitored setting or in the absence of resuscitative equipment[see Warnings and Precautions (5.9)]
- Concurrent use of monoamine oxidase inhibitors (MAOIs) or use of MAOIs within the last 14 days [see Warnings and Precautions (5.10)/Drug Interactions (7)].
- Known or suspected gastrointestinal obstruction, including paralytic ileus [see Warnings and Precautions (5.14)]
- Hypersensitivity or intolerance to aspirin, caffeine, butalbital, or codeine.
- Hemophilia [see Warnings and Precautions (5.19)]
- Reye's Syndrome [see Warnings and Precautions (5.20)]
- Known allergy to nonsteroidal anti-inflammatory drugs (NSAIDs) [see Warnings and Precautions (5.23)]
- Syndrome of asthma, rhinitis, and nasal polyps [see Warnings and Precautions (5.23)]

5 WARNINGS AND PRECAUTIONS

5.1 Addiction, Abuse, and Misuse

BUTALBITAL, ASPIRIN, CAFFEINE and CODEINE PHOSPHATE contains codeine. Codeine in combination with butalbital, aspirin, and caffeine is a Schedule III controlled substance. As BUTALBITAL, ASPIRIN, CAFFEINE and CODEINE PHOSPHATE contains butalbital and codeine, it exposes users to the risks of addiction, abuse, and misuse [see Drug Abuse and Dependence (9)].

Although the risk of addiction in any individual is unknown, it can occur in patients appropriately prescribed BUTALBITAL, ASPIRIN, CAFFEINE and CODEINE PHOSPHATE. Addiction can occur at recommended dosages and if the drug is misused or abused. The risk of opioid-related overdose or overdose-related death is increased with higher opioid doses, and this risk persists over the course of therapy. In postmarketing studies, addiction, abuse, misuse, and fatal and non-fatal opioid overdose were observed in patients with long-term opioid use [see Adverse Reactions (6.2)].

Assess each patient's risk for addiction, abuse, or misuse prior to prescribing BUTALBITAL, ASPIRIN, CAFFEINE and CODEINE PHOSPHATE, and reassess all patients receiving BUTALBITAL, ASPIRIN, CAFFEINE and CODEINE PHOSPHATE for the development of these behaviors and conditions. Risks are increased in patients with a personal or family history of substance abuse (including drug or alcohol abuse or addiction) or mental illness (e.g., major depression). The potential for these risks should not, however, prevent the proper management of pain in any given patient. Patients at increased risk may be prescribed opioids such as BUTALBITAL, ASPIRIN, CAFFEINE and CODEINE PHOSPHATE, but use in such patients necessitates intensive counseling about the risks and proper use of BUTALBITAL, ASPIRIN, CAFFEINE and CODEINE PHOSPHATE along with frequent reevaluation for signs of addiction, abuse, and misuse. Consider recommending or prescribing an opioid overdose reversal agent [see Dosage and Administration (2.2), Warnings and Precautions (5.2)].

Opioids and barbiturates are sought for nonmedical use and are subject to diversion from legitimate prescribed use. Consider these risks when prescribing or dispensing BUTALBITAL, ASPIRIN, CAFFEINE and CODEINE PHOSPHATE. Strategies to reduce these risks include prescribing the drug in the smallest appropriate quantity and advising the patient on careful storage of the drug during the course of treatment and proper disposal of unused drug [see Patient Counseling Information (17)]. Contact local state professional licensing board or state-controlled substances authority for information on how to prevent and detect abuse or diversion of this product.

5.2 Life-Threatening Respiratory Depression

Serious, life-threatening, or fatal respiratory depression has been reported with the use of opioids, even when used as recommended. Respiratory depression, if not immediately recognized and treated, may lead to respiratory arrest and death. Management of respiratory depression may include close observation, supportive measures, and use of opioid overdose reversal agents, depending on the patient's clinical status [see Overdosage (10)].

Carbon dioxide (CO2) retention from opioid-induced respiratory depression can exacerbate the sedating effects of opioids.

While serious, life-threatening, or fatal respiratory depression can occur at any time during the use of BUTALBITAL, ASPIRIN, CAFFEINE and CODEINE PHOSPHATE, the risk is greatest during the initiation of therapy or following a dosage increase.

To reduce the risk of respiratory depression, proper dosing and titration of BUTALBITAL, ASPIRIN, CAFFEINE and CODEINE PHOSPHATE are essential [see Dosage and Administration (2.1)]. Overestimating the BUTALBITAL, ASPIRIN, CAFFEINE and CODEINE PHOSPHATE dosage when converting patients from another opioid product can result in a fatal overdose with the first dose.

Accidental ingestion of BUTALBITAL, ASPIRIN, CAFFEINE and CODEINE PHOSPHATE, especially by children, can result in respiratory depression and death due to an overdose of codeine and butalbital.

Educate patients and caregivers on how to recognize respiratory depression and emphasize the importance of calling 911 or getting emergency medical help right away in the event of a known or suspected overdose [see Patient Counseling Information (17)].

Opioids can cause sleep-related breathing disorders including central sleep apnea (CSA) and sleep-related hypoxemia. Opioid use increases the risk of CSA in a dose-dependent fashion. In patients who present with CSA, consider decreasing the opioid dosage using best practices for opioid taper [see Dosage and Administration (2.4)].

Patient Access to an Opioid Overdose Reversal Agent for the Emergency Treatment of Opioid Overdose

Inform patients and caregivers about opioid overdose reversal agents (e.g., naloxone, nalmefene). Discuss the importance of having access to an opioid overdose reversal agent, especially if the patient has risk factors for overdose (e.g., concomitant use of CNS depressants, a history of opioid use disorder, or prior opioid overdose) or if there are household members (including children) or other close contacts at risk for accidental ingestion or opioid overdose. The presence of risk factors for overdose should not prevent the management of pain in any patient [see Warnings and Precautions (5.1, 5.3)].

Discuss the options for obtaining an opioid overdose reversal agent (e.g., prescription, over-the-counter, or as part of a community-based program).

There are important differences among the opioid overdose reversal agents, such as route of administration, product strength, approved patient age range, and pharmacokinetics. Be familiar with these differences, as outlined in the approved labeling for those products, prior to recommending or prescribing such an agent.

Educate patients and caregivers on how to recognize respiratory depression, and how to use an opioid overdose reversal agent for the emergency treatment of opioid overdose. Emphasize the importance of calling 911 or getting emergency medical help, even if an opioid overdose reversal agent is administered [see Dosage and Administration (2.2), Warnings and Precautions (5.1, 5.3), Overdosage (10)].

5.3 Risks from Concomitant Use with Benzodiazepines or Other CNS Depressants

Profound sedation, respiratory depression, coma, and death may result from the concomitant use of BUTALBITAL, ASPIRIN, CAFFEINE and CODEINE PHOSPHATE with benzodiazepines and/or other CNS depressants, including alcohol (e.g., non-benzodiazepine sedatives/hypnotics, anxiolytics, tranquilizers, muscle relaxants, general anesthetics, antipsychotics, gabapentinoids [gabapentin or pregabalin], and other opioids). Because of these risks, reserve concomitant prescribing of these drugs for use in patients for whom alternative treatment options are inadequate.

Observational studies have demonstrated that concomitant use of opioid analgesics and benzodiazepines increases the risk of drug-related mortality compared to use of opioid analgesics alone. Because of similar pharmacological properties, it is reasonable to expect similar risk with the concomitant use of other CNS depressant drugs with opioid analgesics [see Drug Interactions (7)].

If the decision is made to prescribe a benzodiazepine or other CNS depressant concomitantly with an opioid analgesic, prescribe the lowest effective dosages and minimum durations of concomitant use. In patients already receiving an opioid analgesic, prescribe a lower initial dose of the benzodiazepine or other CNS depressant than indicated in the absence of an opioid, and titrate based on clinical response. If an opioid analgesic is initiated in a patient already taking a benzodiazepine or other CNS depressant, prescribe a lower initial dose of the opioid analgesic, and titrate based on clinical response. Inform patients and caregivers of this potential interaction and educate them on the signs and symptoms of respiratory depression (including sedation).

If concomitant use is warranted, consider recommending or prescribing an opioid overdose reversal agent [see Dosage and Administration (2.2), Warnings and Precautions (5.2), Overdosage (10)].

Advise both patients and caregivers about the risks of respiratory depression and sedation when BUTALBITAL, ASPIRIN, CAFFEINE and CODEINE PHOSPHATE is used with benzodiazepines or other CNS depressants (including alcohol and illicit drugs). Advise patients not to drive or operate heavy machinery until the effects of concomitant use of the benzodiazepine or other CNS depressant have been determined. Screen patients for risk of substance use disorders, including opioid abuse and misuse, and warn them of the risk for overdose and death associated with the use of additional CNS depressants including alcohol and illicit drugs [see Drug Interactions (7) and Patient Counseling Information (17)].

5.4 Neonatal Opioid Withdrawal Syndrome

Use of BUTALBITAL, ASPIRIN, CAFFEINE and CODEINE PHOSPHATE for an extended period of time during pregnancy can result in withdrawal in the neonate. Neonatal opioid withdrawal syndrome, unlike opioid withdrawal syndrome in adults, may be life-threatening if not recognized and treated, and requires management according to protocols developed by neonatology experts. Observe newborns for signs of neonatal opioid withdrawal syndrome and manage accordingly. Advise pregnant women using opioids for an extended period of time of the risk of neonatal opioid withdrawal syndrome and ensure that appropriate treatment will be available [see Use in Specific Populations (8.1, 8.2), Patient Counseling Information (17)].

5.5 Opioid Analgesic Risk Evaluation and Mitigation Strategy (REMS)

To ensure that the benefits of opioid analgesics outweigh the risks of addiction, abuse, and misuse, the Food and Drug Administration (FDA) has required a Risk Evaluation and Mitigation Strategy (REMS) for these products. Under the requirements of the REMS, drug companies with approved opioid analgesic products must make REMS-compliant education programs available to healthcare providers.

Healthcare providers are strongly encouraged to do all of the following:

- Complete a REMS-compliant education program offered by an accredited provider of continuing education (CE) or another education program that includes all the elements of the FDA Education Blueprint for Health Care Providers Involved in the Management or Support of Patients with Pain.
- Discuss the safe use, serious risks, and proper storage and disposal of opioid analgesics with patients and/or their caregivers every time these medicines are prescribed. The Patient Counseling Guide (PCG) can be obtained at this link: www.opioidanalgesicrems.com/patientCounselingGuide.html
- Emphasize to patients and their caregivers the importance of reading the Medication Guide that they will receive from their pharmacist every time an opioid analgesic is dispensed to them.
- Consider using other tools to improve patient, household, and community safety, such as patient prescriber agreements that reinforce patient-prescriber responsibilities.

To obtain further information on the opioid analgesic REMS and for a list of accredited REMS CME/CE, call 1-800-503-0784, or log on to https://www.opioidanalgesicrems.com/home.html The FDA Blueprint can be found at "http://www.fda.gov/OpioidAnalgesicREMSBlueprint".

5.6 Ultra-Rapid Metabolism of Codeine and Other Risk Factors for Life-Threatening Respiratory Depression in Children

Life-threatening respiratory depression and death have occurred in children who received codeine. Codeine is subject to variability in metabolism based upon CYP2D6 genotype (described below), which can lead to an increased exposure to the active metabolite morphine. Based upon postmarketing reports, children younger than 12 years old appear to be more susceptible to the respiratory depressant effects of codeine, particularly if there are risk factors for respiratory depression. For example, many reported cases of death occurred in the post-operative period following tonsillectomy and/or adenoidectomy, and many of the children had evidence of being ultra-rapid metabolizers of codeine. Furthermore, children with obstructive sleep apnea who are treated with codeine for post-tonsillectomy and/or adenoidectomy pain may be particularly sensitive to its respiratory depressant effect. Because of the risk of life-threatening respiratory depression and death:

- BUTALBITAL, ASPIRIN, CAFFEINE and CODEINE PHOSPHATE is contraindicated for all children younger than 12 years of age [see Contraindications (4)].
- BUTALBITAL, ASPIRIN, CAFFEINE and CODEINE PHOSPHATE is contraindicated for post-operative management in pediatric patients younger than 18 years of age following tonsillectomy and/or adenoidectomy [see Contraindications (4)].
- Avoid the use of BUTALBITAL, ASPIRIN, CAFFEINE and CODEINE PHOSPHATE in adolescents 12 to 18 years of age who have other risk factors that may increase their sensitivity to the respiratory depressant effects of codeine unless the benefits outweigh the risks. Risk factors include conditions associated with hypoventilation, such as postoperative status, obstructive sleep apnea, obesity, severe pulmonary disease, neuromuscular disease, and concomitant use of other medications that cause respiratory depression.
- As with adults, when prescribing BUTALBITAL, ASPIRIN, CAFFEINE and CODEINE PHOSPHATE for adolescents, healthcare providers should choose the lowest effective dose for the shortest period of time and inform patients and caregivers about these risks and the signs of morphine overdose [see Use in Specific Populations (8.4), Overdosage (10)].

Nursing Mothers

At least one death was reported in a nursing infant who was exposed to high levels of morphine in breast milk because the mother was an ultra-rapid metabolizer of codeine. Breastfeeding is not recommended during treatment with BUTALBITAL, ASPIRIN, CAFFEINE and CODEINE PHOSPHATE [see Use in Specific Populations (8.2)].

CYP2D6 Genetic Variability: Ultra-rapid metabolizer

Some individuals may be ultra-rapid metabolizers because of a specific CYP2D6 genotype (gene duplications denoted as *1/*1xN or *1/*2xN). The prevalence of this CYP2D6 phenotype varies widely and has been estimated at 1 to 10% for Whites (European, North American), 3 to 4% for Blacks (African Americans), 1 to 2% for East Asians (Chinese, Japanese, Korean), and may be greater than 10% in certain racial/ethnic groups (i.e., Oceanian, Northern African, Middle Eastern, Ashkenazi Jews, Puerto Rican).

These individuals convert codeine into its active metabolite, morphine, more rapidly and completely than other people. This rapid conversion results in higher than expected serum morphine levels. Even at labeled dosage regimens, individuals who are ultra-rapid metabolizers may have life-threatening or fatal respiratory depression or experience signs of overdose (such as extreme sleepiness, confusion, or shallow breathing). [see Overdosage (10)]. Therefore, individuals who are ultra-rapid metabolizers should not use BUTALBITAL, ASPIRIN, CAFFEINE and CODEINE PHOSPHATE.

5.7 Risks of Interactions with Drugs Affecting Cytochrome P450 Isoenzymes

The effects of concomitant use or discontinuation of cytochrome P450 3A4 inducers, 3A4 inhibitors, or 2D6 inhibitors with codeine are complex. Use of cytochrome P450 3A4 inducers, 3A4 inhibitors, or 2D6 inhibitors with BUTALBITAL, ASPIRIN, CAFFEINE and CODEINE PHOSPHATE requires careful consideration of the effects on codeine and the active metabolite, morphine.

- Cytochrome P450 3A4 Interaction
  The concomitant use of BUTALBITAL, ASPIRIN, CAFFEINE and CODEINE PHOSPHATE with all cytochrome P450 3A4 inhibitors, such as macrolide antibiotics (e.g., erythromycin), azole-antifungal agents (e.g., ketoconazole), and protease inhibitors (e.g., ritonavir) or discontinuation of a cytochrome P450 3A4 inducer such as rifampin, carbamazepine, and phenytoin, may result in an increase in codeine plasma concentrations with subsequently greater metabolism by cytochrome P450 2D6, resulting in greater morphine levels, which could increase or prolong adverse reactions and may cause potentially fatal respiratory depression.
  The concomitant use of BUTALBITAL, ASPIRIN, CAFFEINE and CODEINE PHOSPHATE with all cytochrome P450 3A4 inducers or discontinuation of a cytochrome P450 3A4 inhibitor may result in lower codeine levels, greater norcodeine levels, and less metabolism via 2D6 with resultant lower morphine levels. This may be associated with a decrease in efficacy, and in some patients, may result in signs and symptoms of opioid withdrawal.
  Evaluate patients receiving BUTALBITAL, ASPIRIN, CAFFEINE and CODEINE PHOSPHATE and any CYP3A4 inhibitor or inducer at frequent intervals for signs and symptoms that may reflect opioid toxicity and opioid withdrawal when BUTALBITAL, ASPIRIN, CAFFEINE and CODEINE PHOSPHATE is used in conjunction with inhibitors and inducers of CYP3A4.
  If concomitant use of a CYP3A4 inhibitor is necessary or if a CYP3A4 inducer is discontinued, consider dosage reduction of BUTALBITAL, ASPIRIN, CAFFEINE and CODEINE PHOSPHATE until stable drug effects are achieved. Evaluate patients at frequent intervals for respiratory depression and sedation.
  If concomitant use of a CYP3A4 inducer is necessary or if a CYP3A4 inhibitor is discontinued, consider increasing the BUTALBITAL, ASPIRIN, CAFFEINE and CODEINE PHOSPHATE dosage until stable drug effects are achieved. Evaluate patients at frequent intervals for signs of opioid withdrawal. [see Drug Interactions (7)].
- Risks of Concomitant Use or Discontinuation of Cytochrome P450 2D6 Inhibitors
  The concomitant use of BUTALBITAL, ASPIRIN, CAFFEINE and CODEINE PHOSPHATE with all cytochrome P450 2D6 inhibitors (e.g., amiodarone, quinidine) may result in an increase in codeine plasma concentrations and a decrease in active metabolite morphine plasma concentration which could result in an analgesic efficacy reduction or symptoms of opioid withdrawal.
  Discontinuation of a concomitantly used cytochrome P450 2D6 inhibitor may result in a decrease in codeine plasma concentration and an increase in active metabolite morphine plasma concentration which could increase or prolong adverse reactions and may cause potentially fatal respiratory depression.
  Evaluate patients receiving BUTALBITAL, ASPIRIN, CAFFEINE and CODEINE PHOSPHATE and any CYP2D6 inhibitor at frequent intervals for signs and symptoms that may reflect opioid toxicity and opioid withdrawal when BUTALBITAL, ASPIRIN, CAFFEINE and CODEINE PHOSPHATE are used in conjunction with inhibitors of CYP2D6.
  If concomitant use with a CYP2D6 inhibitor is necessary, evaluate patients at frequent intervals for signs of reduced efficacy or opioid withdrawal and consider increasing the BUTALBITAL, ASPIRIN, CAFFEINE and CODEINE PHOSPHATE dosage. After stopping use of a CYP2D6 inhibitor, consider reducing the BUTALBITAL, ASPIRIN, CAFFEINE and CODEINE PHOSPHATE dosage and evaluate patients at frequent intervals for signs and symptoms of respiratory depression or sedation. [see Drug Interactions (7)].

5.8 Opioid-Induced Hyperalgesia and Allodynia

Opioid-Induced Hyperalgesia (OIH) occurs when an opioid analgesic paradoxically causes an increase in pain, or an increase in sensitivity to pain. This condition differs from tolerance, which is the need for increasing doses of opioids to maintain a defined effect [see Dependence (9.3)]. Symptoms of OIH include (but may not be limited to) increased levels of pain upon opioid dosage increase, decreased levels of pain upon opioid dosage decrease, or pain from ordinarily non-painful stimuli (allodynia). These symptoms may suggest OIH only if there is no evidence of underlying disease progression, opioid tolerance, opioid withdrawal, or addictive behavior.

Cases of OIH have been reported, both with short-term and longer-term use of opioid analgesics. Though the mechanism of OIH is not fully understood, multiple biochemical pathways have been implicated. Medical literature suggests a strong biologic plausibility between opioid analgesics and OIH and allodynia. If a patient is suspected to be experiencing OIH, carefully consider appropriately decreasing the dose of the current opioid analgesic or opioid rotation (safely switching the patient to a different opioid moiety) [see Dosage and Administration (2.4); Warnings and Precautions (5.2)].

5.9 Life-Threatening Respiratory Depression in Patients with Chronic Pulmonary Disease or in Elderly, Cachectic, or Debilitated Patients

The use of BUTALBITAL, ASPIRIN, CAFFEINE and CODEINE PHOSPHATE in patients with acute or severe bronchial asthma in an unmonitored setting or in the absence of resuscitative equipment is contraindicated.

Patients with Chronic Pulmonary Disease: BUTALBITAL, ASPIRIN, CAFFEINE and CODEINE PHOSPHATE -treated patients with significant chronic obstructive pulmonary disease or cor pulmonale, and those with a substantially decreased respiratory reserve, hypoxia, hypercapnia, or pre-existing respiratory depression are at increased risk of decreased respiratory drive including apnea, even at recommended dosages of BUTALBITAL, ASPIRIN, CAFFEINE and CODEINE PHOSPHATE [see Warnings and Precautions (5.9)].

Elderly, Cachectic, or Debilitated Patients: Life-threatening respiratory depression is more likely to occur in elderly, cachectic, or debilitated patients because they may have altered pharmacokinetics or altered clearance compared to younger, healthier patients [see Warnings and Precautions (5.9)].

Regularly evaluate patients, particularly when initiating and titrating BUTALBITAL, ASPIRIN, CAFFEINE and CODEINE PHOSPHATE and when BUTALBITAL, ASPIRIN, CAFFEINE and CODEINE PHOSPHATE is given concomitantly with other drugs that depress respiration [see Warnings and Precautions (5.2)]. Alternatively, consider the use of non-opioid analgesics in these patients.

5.10 Interaction with Monoamine Oxidase Inhibitors

Monoamine oxidase inhibitors (MAOIs) may potentiate the effects of morphine, codeine's active metabolite, including respiratory depression, coma, and confusion. BUTALBITAL, ASPIRIN, CAFFEINE and CODEINE PHOSPHATE should not be used in patients taking MAOIs or within 14 days of stopping such treatment.

5.11 Adrenal Insufficiency

Cases of adrenal insufficiency have been reported with opioid use, more often following greater than one month of use. Presentation of adrenal insufficiency may include non-specific symptoms and signs including nausea, vomiting, anorexia, fatigue, weakness, dizziness, and low blood pressure. If adrenal insufficiency is suspected, confirm the diagnosis with diagnostic testing as soon as possible. If adrenal insufficiency is diagnosed, treat with physiologic replacement doses of corticosteroids. Wean the patient off of the opioid to allow adrenal function to recover and continue corticosteroid treatment until adrenal function recovers. Other opioids may be tried as some cases reported use of a different opioid without recurrence of adrenal insufficiency. The information available does not identify any particular opioids as being more likely to be associated with adrenal insufficiency.

5.12 Severe Hypotension

BUTALBITAL, ASPIRIN, CAFFEINE and CODEINE PHOSPHATE may cause severe hypotension including orthostatic hypotension and syncope in ambulatory patients. There is increased risk in patients whose ability to maintain blood pressure has already been compromised by a reduced blood volume or concurrent administration of certain CNS depressant drugs (e.g., phenothiazines or general anesthetics) [see Drug Interactions (7)]. Regularly evaluate these patients for signs of hypotension after initiating or titrating the dosage of BUTALBITAL, ASPIRIN, CAFFEINE and CODEINE PHOSPHATE. In patients with circulatory shock, BUTALBITAL, ASPIRIN, CAFFEINE and CODEINE PHOSPHATE may cause vasodilation that can further reduce cardiac output and blood pressure. Avoid the use of BUTALBITAL, ASPIRIN, CAFFEINE and CODEINE PHOSPHATE in patients with circulatory shock.

5.13 Risks of Use in Patients with Increased Intracranial Pressure, Brain Tumors, Head Injury, or Impaired Consciousness

In patients who may be susceptible to the intracranial effects of CO2 retention (e.g., those with evidence of increased intracranial pressure or brain tumors), BUTALBITAL, ASPIRIN, CAFFEINE and CODEINE PHOSPHATE may reduce respiratory drive, and the resultant CO2 retention can further increase intracranial pressure. Monitor such patients for signs of sedation and respiratory depression, particularly when initiating therapy with BUTALBITAL, ASPIRIN, CAFFEINE and CODEINE PHOSPHATE.

Opioids may also obscure the clinical course in a patient with a head injury. Avoid the use of BUTALBITAL, ASPIRIN, CAFFEINE and CODEINE PHOSPHATE in patients with impaired consciousness or coma.

5.14 Risk of Gastrointestinal Complications

BUTALBITAL, ASPIRIN, CAFFEINE and CODEINE PHOSPHATE is contraindicated in patients with known or suspected gastrointestinal obstruction, including paralytic ileus.

The codeine in BUTALBITAL, ASPIRIN, CAFFEINE and CODEINE PHOSPHATE may cause spasm of the sphincter of Oddi. Opioids may cause increases in serum amylase. Regularly evaluate patients with biliary tract disease, including acute pancreatitis for worsening symptoms.

Cases of opioid-induced esophageal dysfunction (OIED) have been reported in patients taking opioids. The risk of OIED may increase as the dose and/or duration of opioids increases. Regularly evaluate patients for signs and symptoms of OIED (e.g., dysphagia, regurgitation, non-cardiac chest pain)- and, if necessary, adjust opioid therapy as clinically appropriate [see Clinical Pharmacology (12.2)].

Patients with a history of active peptic ulcer disease should avoid using aspirin, which can cause gastric mucosal irritation and bleeding.

The aspirin in BUTALBITAL, ASPIRIN, CAFFEINE and CODEINE PHOSPHATE can cause GI side effects including stomach pain, heartburn, nausea, vomiting, and gross GI bleeding. Although minor upper GI symptoms, such as dyspepsia, are common and can occur anytime during therapy, physicians should remain alert for signs of ulceration and bleeding, even in the absence of previous GI symptoms. Physicians should inform patients about the signs and symptoms of GI side effects and what steps to take if they occur.

5.15 Increased Risk of Seizures in Patients with Seizure Disorders

The codeine in BUTALBITAL, ASPIRIN, CAFFEINE and CODEINE PHOSPHATE may increase the frequency of seizures in patients with seizure disorders, and may increase the risk of seizures occurring in other clinical settings associated with seizures. Regularly evaluate patients with a history of seizure disorders for worsened seizure control during BUTALBITAL, ASPIRIN, CAFFEINE and CODEINE PHOSPHATE therapy.

5.16 Withdrawal

Do not rapidly reduce or abruptly discontinue BUTALBITAL, ASPIRIN, CAFFEINE and CODEINE PHOSPHATE in a patient physically dependent on opioids. Rapid tapering of butalbital, aspirin, caffeine, and codeine phosphate capsules in a patient physically dependent on opioids may lead to a withdrawal syndrome and return of pain [see Dosage and Administration (2.4), Drug Abuse and Dependence (9.3)].

Additionally, avoid the use of mixed agonist/antagonist (e.g., pentazocine, nalbuphine, and butorphanol) or partial agonist (e.g., buprenorphine) analgesics in patients who are receiving a full opioid agonist analgesic, including BUTALBITAL, ASPIRIN, CAFFEINE and CODEINE PHOSPHATE. In these patients, mixed agonist/antagonist and partial agonist analgesics may reduce the analgesic effect and/or precipitate withdrawal symptoms.

When discontinuing BUTALBITAL, ASPIRIN, CAFFEINE and CODEINE PHOSPHATE in a physically-dependent patient, gradually taper the dosage [see Dosage and Administration (2.4)]. Do not abruptly discontinue BUTALBITAL, ASPIRIN, CAFFEINE and CODEINE PHOSPHATE in these patients [see Drug Abuse and Dependence (9.2, 9.3)].

5.17 Fetal Toxicity

Premature Closure of Fetal Ductus Arteriosus

Avoid use of NSAIDs, including BUTALBITAL, ASPIRIN, CAFFEINE and CODEINE PHOSPHATE, in pregnant women at about 30 weeks gestation and later. NSAIDs, including BUTALBITAL, ASPIRIN, CAFFEINE and CODEINE PHOSPHATE, increase the risk of premature closure of the fetal ductus arteriosus at approximately this gestational age.

Oligohydramnios/Neonatal Renal Impairment

Use of NSAIDs, including BUTALBITAL, ASPIRIN, CAFFEINE and CODEINE PHOSPHATE, at about 20 weeks gestation or later in pregnancy may cause fetal renal dysfunction leading to oligohydramnios and, in some cases, neonatal renal impairment. These adverse outcomes are seen, on average, after days to weeks of treatment, although oligohydramnios has been infrequently reported as soon as 48 hours after NSAID initiation. Oligohydramnios is often, but not always, reversible with treatment discontinuation. Complications of prolonged oligohydramnios may, for example, include limb contractures and delayed lung maturation. In some postmarketing cases of impaired neonatal renal function, invasive procedures such as exchange transfusion or dialysis were required.

If NSAID treatment is necessary between about 20 weeks and 30 weeks gestation, limit BUTALBITAL, ASPIRIN, CAFFEINE and CODEINE PHOSPHATE use to the lowest effective dose and shortest duration possible. Consider ultrasound monitoring of amniotic fluid if BUTALBITAL, ASPIRIN, CAFFEINE and CODEINE PHOSPHATE treatment extends beyond 48 hours. Discontinue BUTALBITAL, ASPIRIN, CAFFEINE and CODEINE PHOSPHATE if oligohydramnios occurs and follow up according to clinical practice [see Use in Specific Populations (8.1)].

5.18 Risks of Driving and Operating Machinery

BUTALBITAL, ASPIRIN, CAFFEINE and CODEINE PHOSPHATE may impair the mental or physical abilities needed to perform potentially hazardous activities such as driving a car or operating machinery. Warn patients not to drive or operate dangerous machinery unless they are tolerant to the effects of BUTALBITAL, ASPIRIN, CAFFEINE and CODEINE PHOSPHATE and know how they will react to the medication.

5.19 Coagulation Abnormalities and Bleeding Risks

Even low doses of aspirin can inhibit platelet function leading to an increase in bleeding time. This can adversely affect patients with inherited (i.e. hemophilia) or acquired (i.e. liver disease or vitamin K deficiency) bleeding disorders. Aspirin is contraindicated in patients with hemophilia.

Aspirin administered pre-operatively may prolong the bleeding time.

Patients who consume three or more alcoholic drinks every day should be counseled about the bleeding risks involved with chronic, heavy alcohol use while taking aspirin.

5.20 Reye's Syndrome

Aspirin should not be used in children or teenagers for viral infections, with or without fever, because of the risk of Reye's syndrome with concomitant use of aspirin in certain viral illnesses.

5.21 Serious Skin Reactions

NSAIDs, including aspirin, a component of BUTALBITAL, ASPIRIN, CAFFEINE and CODEINE PHOSPHATE, can cause serious skin adverse reactions such as exfoliative dermatitis, Stevens-Johnson Syndrome (SJS), and toxic epidermal necrolysis (TEN), which can be fatal. NSAIDs can also cause fixed drug eruption (FDE). FDE may present as a more severe variant known as generalized bullous fixed drug eruption (GBFDE), which can be life-threatening. These serious events may occur without warning. Inform patients about the signs and symptoms of serious skin reactions, and to discontinue the use of BUTALBITAL, ASPIRIN, CAFFEINE and CODEINE PHOSPHATE at the first appearance of skin rash or any other sign of hypersensitivity. BUTALBITAL, ASPIRIN, CAFFEINE and CODEINE PHOSPHATE is contraindicated in patients with previous serious skin reactions to NSAIDs [see CONTRAINDICATIONS (4)].

5.22 Drug Reaction with Eosinophilia and Systemic Symptoms (DRESS)

Drug Reaction with Eosinophilia and Systemic Symptoms (DRESS) has been reported in patients taking NSAIDs such as BUTALBITAL, ASPIRIN, CAFFEINE and CODEINE PHOSPHATE. Some of these events have been fatal or life threatening. DRESS typically, although not exclusively, presents with fever, rash, lymphadenopathy, and/or facial swelling. Other clinical manifestations may include hepatitis, nephritis, hematological abnormalities, myocarditis, or myositis. Sometimes symptoms of DRESS may resemble an acute viral infection. Eosinophilia is often present. Because this disorder is variable in its presentation, other organ systems not noted here may be involved. It is important to note that early manifestations of hypersensitivity, such as fever or lymphadenopathy, may be present even though rash is not evident. If such signs or symptoms are present, discontinue BUTALBITAL, ASPIRIN, CAFFEINE and CODEINE PHOSPHATE and evaluate the patient immediately.

5.23 Allergy

Aspirin is contraindicated in patients with known allergy to nonsteroidal anti-inflammatory drug products (NSAIDs) and in patients with the syndrome of asthma, rhinitis, and nasal polyps. Aspirin may cause severe urticaria, angioedema, or bronchospasm (asthma).

5.24 Drug/Laboratory Test Interactions

Aspirin: Aspirin may interfere with the following laboratory determinations in blood: serum amylase, fasting blood glucose, cholesterol, protein, serum glutamic-oxalacetic transaminase (SGOT), uric acid, prothrombin time and bleeding time. Aspirin may interfere with the following laboratory determinations in urine: glucose, 5-hydroxy-indoleacetic acid, Gerhardt ketone, vanillylmandelic acid (VMA), uric acid, diacetic acid, and spectrophotometric detection of barbiturates.

Codeine: Codeine may increase serum amylase levels.

6 ADVERSE REACTIONS

The following serious adverse reactions are described, or described in greater detail, in other sections:

- Addiction, Abuse, and Misuse [see Warnings and Precautions (5.1)]
- Life-Threatening Respiratory Depression [see Warnings and Precautions ((5.2)
- Risks from Concomitant Use with Benzodiazepines or Other CNS Depressants [see Warnings and Precautions (5.3)
- Ultra-Rapid Metabolism of Codeine and Other Risk Factors for Life-Threatening Respiratory Depression in Children [see Warnings and Precautions (5.6)]
- Neonatal Opioid Withdrawal Syndrome [see Warnings and Precautions (5.4)]
- Opioid-Induced Hyperalgesia and Allodynia [see Warnings and Precautions (5.8)]
- Adrenal Insufficiency [see Warnings and Precautions (5.11)]
- Severe Hypotension [see Warnings and Precautions (5.12)]
- Risks of Use in Patients with Gastrointestinal Conditions Including Peptic Ulcer Disease [see Warnings and Precautions (5.14)]
- Increased Risk of Seizures in Patients with Seizure Disorders [see Warnings and Precautions (5.15)]
- Withdrawal [see Warnings and Precautions (5.16)]
- Coagulation Abnormalities and Bleeding Risks [see Warnings and Precautions (5.19)]
- Reye's Syndrome [see Warnings and Precautions (5.20)]
- Serious Skin Reactions [see Warnings and Precautions (5.21)]
- Allergy [see Warnings and Precautions (5.23)]

6.1 Clinical Trials Experience

Because clinical trials are conducted under widely varying conditions, adverse reaction rates observed in the clinical trials of a drug cannot be directly compared to rates in the clinical trials of another drug and may not reflect the rates observed in practice.

Incidence in Controlled Clinical Trials

The following table summarizes the incidence rates of the adverse events reported by at least 1% of the BUTALBITAL, ASPIRIN, CAFFEINE and CODEINE PHOSPHATE treated patients in controlled clinical trials comparing BUTALBITAL, ASPIRIN, CAFFEINE and CODEINE PHOSPHATE to placebo, and provides a comparison to the incidence rates reported by the placebo-treated patients.

The prescriber should be aware that these figures cannot be used to predict the incidence of side effects in the course of usual medical practice where patient characteristics and other factors differ from those that prevailed in the clinical trials. Similarly, the cited frequencies cannot be compared with figures obtained from other clinical investigations involving different treatments, uses, and investigators.

Table 1:Adverse Events Reported by at least 1% of BUTALBITAL, ASPIRIN, CAFFEINE and CODEINE PHOSPHATE Treated Patients During Placebo Controlled Clinical Trials Incidence Rate of Adverse Events
Body System/Adverse Event | BUTALBITAL, ASPIRIN, CAFFEINE and CODEINE PHOSPHATE (N=382) | Placebo (N =377)
Central Nervous
Drowsiness | 2.4% | 0.5%
Dizziness/Lightheadedness | 2.6% | 0.5%
Intoxicated Feeling | 1.0% | 0%
Gastrointestinal
Nausea/Abdominal Pain | 3.7% | 0.8%

Other Adverse Events Reported During Controlled Clinical Trials

The listing that follows represents the proportion of the 382 patients exposed to BUTALBITAL, ASPIRIN, CAFFEINE and CODEINE PHOSPHATE while participating in the controlled clinical trials who reported, on at least one occasion, an adverse event of the type cited. All reported adverse events, except those already presented in the previous table, are included. It is important to emphasize that, although the adverse events reported did occur while the patient was receiving BUTALBITAL, ASPIRIN, CAFFEINE and CODEINE PHOSPHATE, the adverse events were not necessarily caused by BUTALBITAL, ASPIRIN, CAFFEINE and CODEINE PHOSPHATE.

Adverse events are classified by body system and frequency. “Frequent” is defined as an adverse event which occurred in at least 1/100 (1%) of the patients; all adverse events listed in the previous table are frequent. “Infrequent” is defined as an adverse event that occurred in less than 1/100 patients but at least 1/1000 patients. All adverse events tabulated below are classified as infrequent.

Central Nervous: headache, shaky feeling, tingling, agitation, fainting, fatigue, heavy eyelids, high energy, hot spells, numbness, and sluggishness.

Autonomic Nervous: dry mouth and hyperhidrosis.

Gastrointestinal: vomiting, difficulty swallowing, and heartburn.

Cardiovascular: tachycardia.

Musculoskeletal: leg pain and muscle fatigue.

Genitourinary: diuresis.

Miscellaneous: pruritus, fever, earache, nasal congestion, and tinnitus.

The following adverse drug reactions have been reported with the components of BUTALBITAL, ASPIRIN, CAFFEINE and CODEINE PHOSPHATE. Potential effects of high dosage are listed in the [see Overdosage (10)] section of this insert.

Aspirin: occult blood loss, hemolytic anemia, iron deficiency anemia, gastric distress, heartburn, nausea, peptic ulcer, prolonged bleeding time, acute airway obstruction, renal toxicity when taken in high doses for prolonged periods, impaired urate excretion, hepatitis.

Caffeine: cardiac stimulation, irritability, tremor, dependence, nephrotoxicity, hyperglycemia.

Codeine: nausea, vomiting, drowsiness, lightheadedness, constipation, pruritus.

6.2 Postmarketing Experience

The following adverse reactions have been identified during post approval use of BUTALBITAL, ASPIRIN, CAFFEINE and CODEINE PHOSPHATE. Because these reactions are reported voluntarily from a population of uncertain size, it is not always possible to reliably estimate their frequency or establish a causal relationship to drug exposure.

Central Nervous: abuse, addiction, anxiety, depression, disorientation, hallucination, hyperactivity, insomnia, libido decrease, nervousness, neuropathy, psychosis, sedation, sexual activity increase, slurred speech, twitching, unconsciousness, vertigo.

Autonomic Nervous: epistaxis, flushing, miosis, salivation.

Gastrointestinal: anorexia, appetite increased, constipation, diarrhea, esophagitis, gastroenteritis, gastrointestinal spasm, hiccup, mouth burning, pyloric ulcer.

Cardiovascular: chest pain, hypotensive reaction, palpitations, syncope.

Skin: erythema, erythema multiforme, exfoliative dermatitis, Stevens-Johnson Syndrome (SJS), hives, rash, toxic epidermal necrolysis, and fixed drug eruption (FDE).

Urinary: kidney impairment, urinary difficulty.

Miscellaneous: allergic reaction, anaphylactic shock, cholangiocarcinoma, drug interaction with erythromycin (stomach upset), edema.

Serotonin syndrome: Cases of serotonin syndrome, a potentially life-threatening condition, have been reported during concomitant use of opioids with serotonergic drugs.

Adrenal insufficiency: Cases of adrenal insufficiency have been reported with opioid use, more often following greater than one month of use.

Anaphylaxis: Anaphylaxis has been reported with ingredients contained in BUTALBITAL, ASPIRIN, CAFFEINE and CODEINE PHOSPHATE.

Androgen deficiency: Cases of androgen deficiency have occurred with use of opioidsfor an extended period of time. [see Clinical Pharmacology (12.2)].

Hyperalgesia and Allodynia: Cases of hyperalgesia and allodynia have been reported with opioid therapy of any duration [see Warnings and Precautions (5.8)]

Hypoglycemia: Cases of hypoglycemia have been reported in patients taking opioids. Most reports were in patients with at least one predisposing risk factor (e.g., diabetes).

Opioid-induced esophageal dysfunction (OIED): Cases of OIED have been reported in patients taking opioids and may occur more frequently in patients taking higher doses of opioids, and/or in patients taking opioids longer term [see Warnings and Precautions (5.14)].

Adverse Reactions from Observational Studies

A prospective, observational cohort study estimated the risks of addiction, abuse, and misuse in patients initiating long-term use of Schedule II opioid analgesics between 2017 and 2021. Study participants included in one or more analyses had been enrolled in selected insurance plans or health systems for at least one year, were free of at least one outcome at baseline, completed a minimum number of follow-up assessments, and either: 1) filled multiple extended-release/long-acting opioid analgesic prescriptions during a 90 day period (n=978); or 2) filled any Schedule II opioid analgesic prescriptions covering at least 70 of 90 days (n=1,244). Those included also had no dispensing of the qualifying opioids in the previous 6 months.

Over 12 months:

- approximately 1% to 6% of participants across the two cohorts newly met criteria for addiction, as assessed with two validated interviewbased measures of moderate-to-severe opioid use disorder based on Diagnostic and Statistical Manual of Mental Disorders, Fifth Edition (DSM-5) criteria, and
- approximately 9% and 22% of participants across the two cohorts newly met criteria for prescription opioid abuse and misuse [defined in Drug Abuse and Dependence (9.2)], respectively, as measured with a validated self-reported instrument.

A retrospective, observational cohort study estimated the risk of opioid-involved overdose or opioid overdose-related death in patients with new long-term use of Schedule II opioid analgesics from 2006 through 2016 (n=220,249). Included patients had been enrolled in either one of two commercial insurance programs, one managed care program, or one Medicaid program for at least 9 months. New long-term use was defined as having Schedule II opioid analgesic prescriptions covering at least 70 days' supply over the 3 months prior to study entry and none during the preceding 6 months. Patients were excluded if they had an opioid-involved overdose in the 9 months prior to study entry. Overdose was measured using a validated medical code-based algorithm with linkage to the National Death Index database. The 5-year cumulative incidence estimates for opioid-involved overdose or opioid overdose-related death ranged from approximately 1.5% to 4% across study sites, counting only the first event during follow-up. Approximately 17% of first opioid overdoses observed over the entire study period (5-11 years, depending on the study site) were fatal. Higher baseline opioid dose was the strongest and most consistent predictor of opioid-involved overdose or opioid overdose-related death. Study exclusion criteria may have selected patients at lower risk of overdose, and substantial loss to follow-up (approximately 80%) also may have biased estimates.

The risk estimates from the studies described above may not be generalizable to all patients receiving opioid analgesics, such as those with exposures shorter or longer than the duration evaluated in the studies.

7 DRUG INTERACTIONS

Table 2 includes clinically significant drug interactions with BUTALBITAL, ASPIRIN, CAFFEINE and CODEINE PHOSPHATE.

Table 2: Clinically Significant Drug Interactions With BUTALBITAL, ASPIRIN, CAFFEINE And CODEINE PHOSPHATE
Inhibitors of CYP3A4
Clinical Impact: | The concomitant use of BUTALBITAL, ASPIRIN, CAFFEINE and CODEINE PHOSPHATE with CYP3A4 inhibitors may result in an increase in codeine plasma concentrations with subsequently greater metabolism by cytochrome CYP2D6, resulting in greater morphine levels, which could increase or prolong adverse reactions and may cause potentially fatal respiratory depression, particularly when an inhibitor is added after a stable dose of BUTALBITAL, ASPIRIN, CAFFEINE and CODEINE PHOSPHATE is achieved. After stopping a CYP3A4 inhibitor, as the effects of the inhibitor decline, it may result in lower codeine levels, greater norcodeine levels, and less metabolism via 2D6 with resultant lower morphine levels [see Clinical Pharmacology (12.3)], resulting in decreased opioid efficacy or a withdrawal syndrome in patients who had developed physical dependence to codeine.
Intervention: | If concomitant use with a CYP3A4 inhibitor is necessary, consider dosage reduction of BUTALBITAL, ASPIRIN, CAFFEINE and CODEINE PHOSPHATE until stable drug effects are achieved. Evaluate patients at frequent intervals for respiratory depression and sedation. If a CYP3A4 inhibitor is discontinued, consider increasing the BUTALBITAL, ASPIRIN, CAFFEINE and CODEINE PHOSPHATE dosage until stable drug effects are achieved. Evaluate for signs of opioid withdrawal.
Examples | Macrolide antibiotics (e.g., erythromycin), azole-antifungal agents (e.g. ketoconazole), protease inhibitors (e.g., ritonavir)
CYP3A4 Inducers
Clinical Impact: | The concomitant use of BUTALBITAL, ASPIRIN, CAFFEINE and CODEINE PHOSPHATE and CYP3A4 inducers can result in lower codeine levels, greater norcodeine levels, and less metabolism via 2D6 with resultant lower morphine levels [see Clinical Pharmacology (12.3)], resulting in decreased efficacy or onset of a withdrawal syndrome in patients who have developed physical dependence [see Warnings and Precautions (5.16)]. After stopping a CYP3A4 inducer, as the effects of the inducer decline, the codeine plasma concentration may increase with subsequently greater metabolism by cytochrome CYP2D6, resulting in greater morphine levels [see Clinical Pharmacology (12.3)], which could increase or prolong both the therapeutic effects and adverse reactions, and may cause serious respiratory depression.
Intervention: | If concomitant use of a CYP3A4 inducer is necessary, evaluate patients at frequent intervals for reduced efficacy and signs of opioid withdrawal and consider increasing the BUTALBITAL, ASPIRIN, CAFFEINE and CODEINE PHOSPHATE dosage as needed. If a CYP3A4 inducer is discontinued, consider BUTALBITAL, ASPIRIN, CAFFEINE and CODEINE PHOSPHATE dosage reduction, and evaluate patients at frequent intervals for signs of respiratory depression and sedation.
Examples | Rifampin, carbamazepine, phenytoin
Inhibitors of CYP2D6
Clinical Impact: | Codeine in BUTALBITAL, ASPIRIN, CAFFEINE and CODEINE PHOSPHATE is metabolized by CYP2D6 to form morphine. The concomitant use of BUTALBITAL, ASPIRIN, CAFFEINE and CODEINE PHOSPHATE and CYP2D6 inhibitors can increase the plasma concentration of codeine, but can decrease the plasma concentrations of active metabolite morphine which could result in reduced analgesic efficacy or symptoms of opioid withdrawal, particularly when an inhibitor is added after a stable dose of BUTALBITAL, ASPIRIN, CAFFEINE and CODEINE PHOSPHATE is achieved [see Clinical Pharmacology (12.3)]. After stopping a CYP2D6 inhibitor, as the effects of the inhibitor decline, the codeine plasma concentration will decrease but the active metabolite morphine plasma concentration will increase, which could increase or prolong adverse reactions and may cause potentially fatal respiratory depression [see Clinical Pharmacology (12.3)].
Intervention: | If concomitant use with a CYP2D6 inhibitor is necessary, or if a CYP2D6 inhibitor is discontinued after concomitant use, consider dosage adjustment of BUTALBITAL, ASPIRIN, CAFFEINE and CODEINE PHOSPHATE and evaluate patients at frequent intervals. If concomitant use with CYP2D6 inhibitors is necessary, evaluate patients for reduced efficacy or signs and symptoms of opioid withdrawal and consider increasing the dose of BUTALBITAL, ASPIRIN, CAFFEINE and CODEINE PHOSPHATE as needed. After stopping use of a CYP2D6 inhibitor, consider reducing the dose of BUTALBITAL, ASPIRIN, CAFFEINE and CODEINE PHOSPHATE and evaluate patients at frequent intervals for signs and symptoms of respiratory depression or sedation.
Examples | paroxetine, fluoxetine, bupropion, quinidine
Benzodiazepines and other Central Nervous System (CNS) Depressants
Clinical Impact: | Due to additive pharmacologic effect, the concomitant use of benzodiazepines or other CNS depressants including alcohol, increases the risk of respiratory depression, profound sedation, coma, and death.
Intervention: | Reserve concomitant prescribing of these drugs for use in patients for whom alternative treatment options are inadequate. Limit dosages and durations to the minimum required. Inform patients and caregivers of this potential interaction and educate them on the signs and symptoms of respiratory depression (including sedation). If concomitant use is warranted, consider recommending or prescribing an opioid overdose reversal agent [see Dosage and Administration (2.2), Warnings and Precautions (5.1, 5.2, 5.3)].
Examples: | Benzodiazepines and other sedatives/hypnotics, anxiolytics, tranquilizers, muscle relaxants, general anesthetics, antipsychotics, gabapentinoids (gabapentin or pregabalin), other opioids, alcohol.
Serotonergic Drugs
Clinical Impact: | The concomitant use of opioids with other drugs that affect the serotonergic neurotransmitter system has resulted in serotonin syndrome.
Intervention: | If concomitant use is warranted, frequently evaluate the patient, particularly during treatment initiation and dose adjustment. Discontinue BUTALBITAL, ASPIRIN, CAFFEINE and CODEINE PHOSPHATE immediately if serotonin syndrome is suspected.
Examples: | Selective serotonin reuptake inhibitors (SSRIs), serotonin and norepinephrine reuptake inhibitors (SNRIs), tricyclic antidepressants (TCAs), triptans, 5-HT3 receptor antagonists, drugs that effect the serotonin neurotransmitter system (e.g., mirtazapine, trazodone, tramadol), certain muscle relaxants (i.e.,cyclobenzaprine, metaxalone), monoamine oxidase (MAO) inhibitors (those intended to treat psychiatric disorders and also others, such as linezolid and intravenous methylene blue).
Monoamine Oxidase Inhibitors (MAOIs)
Clinical Impact: | MAOI interactions with opioids may manifest as serotonin syndrome or opioid toxicity (e.g., respiratory depression, coma) [see Warnings and Precautions (5.10)].
Intervention: | Do not use BUTALBITAL, ASPIRIN, CAFFEINE and CODEINE PHOSPHATE in patients taking MAOIs or within 14 days of stopping such treatment. If urgent use of an opioid is necessary, use test doses and frequent titration of small doses of other opioids (such as oxycodone, hydrocodone, oxymorphone, hydrocodone, or buprenorphine) to treat pain while closely monitoring blood pressure and signs and symptoms of CNS and respiratory depression.
Examples: | Phenelzine, tranylcypromine, linezolid
Mixed Agonist/Antagonist and Partial Agonist Opioid Analgesics
Clinical Impact: | May reduce the analgesic effect of BUTALBITAL, ASPIRIN, CAFFEINE and CODEINE PHOSPHATE and/or precipitate withdrawal symptoms.
Intervention: | Avoid concomitant use.
Examples: | Butorphanol, nalbuphine, pentazocine, buprenorphine,
Muscle Relaxants
Clinical Impact: | Codeine may enhance the neuromuscular blocking action of skeletal muscle relaxants and produce an increased degree of respiratory depression.
Intervention: | Because respiratory depression may be greater than otherwise expected, decrease the dosage of BUTALBITAL, ASPIRIN, CAFFEINE and CODEINE PHOSPHATE and/or the muscle relaxant as necessary. Due to the risk of respiratory depression with concomitant use of skeletal muscle relaxants and opioids, consider recommending or prescribing an opioid overdose reversal agent [see Dosage and Administration (2.2), Warnings and Precautions (5.2, 5.3)].
Examples: | Cyclobenzaprine, metaxalone.
Diuretics
Clinical Impact: | Opioids can reduce the efficacy of diuretics by inducing the release of antidiuretic hormone.
Intervention: | Evaluate patients for signs of diminished diuresis and/or effects on blood pressure and increase the dosage of the diuretic as needed. The effectiveness of diuretics in patients with underlying renal or cardiovascular disease may be diminished by the concomitant administration of aspirin due to inhibition of renal prostaglandins, leading to decreased renal blood flow and salt and fluid retention.
Anticholinergic Drugs
Clinical Impact: | The concomitant use of anticholinergic drugs may increase risk of urinary retention and/or severe constipation, which may lead to paralytic ileus.
Intervention: | Evaluate patients for signs of urinary retention or reduced gastric motility when BUTALBITAL, ASPIRIN, CAFFEINE and CODEINE PHOSPHATE is used concomitantly with anticholinergic drugs.
Anticoagulants
Clinical Impact: | Aspirin may enhance the effects of anticoagulants. Concurrent use may increase the risk of bleeding. Aspirin can also displace warfarin from protein binding sides, leading to prolongation of both the prothrombin time and the bleeding time.
Intervention: | Evaluate patients for signs of bleeding.
Examples: | Warfarin, heparin, enoxaparin, clopidogrel, prasugrel, rivaroxaban, apixaban
Uricosuric Agents
Clinical Impact: | Aspirin inhibits the uricosuric effects of uricosuric agents.
Intervention: | Avoid concomitant use.
Examples: | Probenecid
Carbonic Anhydrase Inhibitors
Clinical Impact: | Concurrent use with aspirin can lead to high serum concentrations of the carbonic anhydrase inhibitor and cause toxicity due to competition at the renal tubule for secretion.
Intervention: | Consider reducing the dose of the carbonic anhydrase inhibitor and evaluate patient for any adverse effects from the carbonic anhydrase inhibitor.
Examples: | Acetazolamide, methazolamide
Methotrexate
Clinical Impact: | Aspirin may enhance the toxicity of methotrexate by displacing it from its plasma protein binding sites and/or reducing its renal clearance.
Intervention: | Use caution if using concomitantly, especially in elderly patients or patients with renal impairment. Evaluate patients for methotrexate toxicity.
Nephrotoxic Agents
Clinical Impact: | Concomitant use with aspirin may lead to additive nephrotoxicity due to the inhibition of renal prostaglandins by aspirin. Also, the plasma concentration of aspirin is increased by conditions that reduce the glomerular filtration rate or tubular secretion.
Intervention: | Use BUTALBITAL, ASPIRIN, CAFFEINE and CODEINE PHOSPHATE with caution if used concomitantly with nephrotoxic agents. Closely evaluate the renal function of patients
Examples: | Aminoglycosides, amphotericin B, systemic bacitracin, cisplatin, cyclosporine, foscarnet, or parenteral vancomycin
Angiotensin Converting Enzyme (ACE) Inhibitors
Clinical Impact: | The hyponatremic and hypotensive effects of ACE inhibitors may be diminished by the concomitant administration of aspirin due to its indirect effect on the renin-angiotensin conversion pathway.
Intervention: | Use caution if using concomitantly. Evaluate the blood pressure and renal function of patients.
Examples: | Ramipril, captopril
Beta Blockers
Clinical Impact: | The hypotensive effects of beta blockers may be diminished by the concomitant administration of aspirin due to inhibition of renal prostaglandins, leading to decreased renal blood flow, and salt and fluid retention.
Intervention: | Use caution if using concomitantly. Evaluate the blood pressure and renal function of patients
Examples: | Metoprolol, propranolol
Hypoglycemic Agents
Clinical Impact: | Aspirin may increase the serum glucose-lowering action of insulin and sulfonylureas leading to hypoglycemia.
Intervention: | Patients should be advised to consult a physician if any signs or symptoms of hypoglycemia occur.
Examples: | Insulin, glimepiride, glipizide
Anticonvulsants
Clinical Impact: | Aspirin can displace protein-bound phenytoin and valproic acid, leading to a decrease in the total concentration of phenytoin and an increase in serum valproic acid levels.
Intervention: | Use caution if using concomitantly.
Examples: | Phenytoin, valproic acid
Nonsteroidal Anti-inflammatory Drugs (NSAIDs)
Clinical Impact: | Concurrent use with aspirin may increase the risk of bleeding or lead to decreased renal function. Aspirin may enhance serious side effects and toxicity of ketorolac by displacing it from its plasma protein binding sites and/or reducing its renal clearance.
Intervention: | Avoid concomitant use.
Examples: | Ketorolac, ibuprofen, naproxen, diclofenac
Corticosteroids
Clinical Impact: | In patients receiving concomitant corticosteroids and chronic use of aspirin, withdrawal of corticosteroids may result in salicylism because corticosteroids enhance renal clearance of salicylates and their withdrawal is followed by return to normal rates of renal clearance.
Intervention: | Avoid concomitant use

8 USE IN SPECIFIC POPULATIONS

8.1 Pregnancy

Risk Summary

Use of opioid analgesics for an extended period of time during pregnancy may cause neonatal opioid withdrawal syndrome. [see Warnings and Precautions (5.4)]. Use of NSAIDS, including aspirincan cause premature closure of the fetal ductus arteriosus and fetal renal dysfunction leading to oligohydramnios and, in some cases, neonatal renal impairment. Because of these risks, limit dose and duration of BUTALBITAL, ASPIRIN, CAFFEINE and CODEINE PHOSPHATE use between about 20 and 30 weeks of gestation, and avoid BUTALBITAL, ASPIRIN, CAFFEINE and CODEINE PHOSPHATE use at about 30 weeks of gestation and later in pregnancy [see Clinical Considerations, Data].

Premature Closure of Fetal Ductus Arteriosus

Use of NSAIDs, including aspirin, at about 30 weeks gestation or later in pregnancy increases the risk of premature closure of the fetal ductus arteriosus.

Oligohydramnios/Neonatal Renal Impairment

Use of NSAIDs at about 20 weeks gestation or later in pregnancy has been associated with cases of fetal renal dysfunction leading to oligohydramnios, and in some cases, neonatal renal impairment.

Animal reproduction studies have not been conducted with the combination of butalbital, aspirin, caffeine, and codeine phosphate capsules or with butalbital alone.

In animal reproduction studies, codeine administration during organogenesis has been shown to produce delayed ossification in the offspring of mice at 2.8 times maximum recommended human dose (MRHD) of 180 mg/day, embryolethal and fetotoxic effects in the offspring of rats and hamsters at approximately 4 to 6 times the MRHD, and cranial malformations/ cranioschisis in the offspring of hamsters between 2 and 8 times the MRHD [see Data].

Based on animal data, prostaglandins have been shown to have an important role in endometrial vascular permeability, blastocyst implantation and decidualization. In animal studies, administration of prostaglandin synthesis inhibitors such as aspirin, resulted in increased pre-and post-implantation loss. Prostaglandins also have been shown to have an important role in fetal kidney development. In published animal studies, prostaglandin synthesis inhibitors have been reported to impair kidney development when administered at clinically relevant doses.

The estimated background risk of major birth defects and miscarriage for the indicated population(s) is unknown. All pregnancies have a background risk of birth defect, loss, or other adverse outcomes. In the U.S. general population, the estimated background risk of major birth defects and miscarriage in clinically recognized pregnancies is 2-4% and 15-20%, respectively.

Clinical Considerations

Fetal/Neonatal Adverse Reactions

Use of opioid analgesics for an extended period of time during pregnancy for medical or nonmedical purposes can result in physical dependence in the neonate and neonatal opioid withdrawal syndrome shortly after birth.

Neonatal opioid withdrawal syndrome presents as irritability, hyperactivity and abnormal sleep pattern, high pitched cry, tremor, vomiting, diarrhea and failure to gain weight. The onset, duration, and severity of neonatal opioid withdrawal syndrome vary based on the specific opioid used, duration of use, timing and amount of last maternal use, and rate of elimination of the drug by the newborn. Observe newborns for symptoms of neonatal opioid withdrawal syndrome and manage accordingly [see Warnings and Precautions (5.4)].

Premature Closure of Fetal Ductus Arteriosus:

Avoid use of NSAIDs in women at about 30 weeks gestation and later in pregnancy, because NSAIDs, including BUTALBITAL, ASPIRIN, CAFFEINE and CODEINE PHOSPHATE, can cause premature closure of the fetal ductus arteriosus [see Data].

Oligohydramnios/Neonatal Renal Impairment:

If an NSAID is necessary at about 20 weeks gestation or later in pregnancy, limit the use to the lowest effective dose and shortest duration possible. If BUTALBITAL, ASPIRIN, CAFFEINE and CODEINE PHOSPHATE treatment extends beyond 48 hours, consider monitoring with ultrasound for oligohydramnios. If oligohydramnios occurs, discontinue BUTALBITAL, ASPIRIN, CAFFEINE and CODEINE PHOSPHATE and follow up according to clinical practice [see Data].

Labor or Delivery

There are no studies on the effects of BUTALBITAL, ASPIRIN, CAFFEINE and CODEINE PHOSPHATE during labor or delivery. In animal studies, NSAIDS, including aspirin, inhibit prostaglandin synthesis, caused delayed parturition, and increase the incidence of stillbirth.

Opioids cross the placenta and may produce respiratory depression and psycho-physiologic effects in neonates. An opioid overdose reversal agent, such as naloxone or nalmefene, must be available for reversal of opioid-induced respiratory depression in the neonate. BUTALBITAL, ASPIRIN, CAFFEINE and CODEINE PHOSPHATE is not recommended for use in pregnant women during or immediately prior to labor, when other analgesic techniques are more appropriate. Opioid analgesics, including BUTALBITAL, ASPIRIN, CAFFEINE and CODEINE PHOSPHATE, can prolong labor through actions which temporarily reduce the strength, duration, and frequency of uterine contractions. However, this effect is not consistent and may be offset by an increased rate of cervical dilation, which tends to shorten labor. Monitor neonates exposed to opioid analgesics during labor for signs of excess sedation and respiratory depression.

Aspirin should be avoided one week prior to and during labor and delivery because it can result in excessive blood loss at delivery. Prolonged gestation and prolonged labor due to prostaglandin inhibition have been reported.

Data

Human Data

Premature Closure of Fetal Ductus Arteriosus:

Published literature reports that the use of NSAIDs at about 30 weeks of gestation and later in pregnancy may cause premature closure of the fetal ductus arteriosus.

Oligohydramnios/Neonatal Renal Impairment:

Published studies and postmarketing reports describe maternal NSAID use at about 20 weeks gestation or later in pregnancy associated with fetal renal dysfunction leading to oligohydramnios, and in some cases, neonatal renal impairment. These adverse outcomes are seen, on average, after days to weeks of treatment, although oligohydramnios has been infrequently reported as soon as 48 hours after NSAID initiation. In many cases, but not all, the decrease in amniotic fluid was transient and reversible with cessation of the drug. There have been a limited number of case reports of maternal NSAID use and neonatal renal dysfunction without oligohydramnios, some of which were irreversible. Some cases of neonatal renal dysfunction required treatment with invasive procedures, such as exchange transfusion or dialysis.

Methodological limitations of these postmarketing studies and reports include lack of a control group; limited information regarding dose, duration, and timing of drug exposure; and concomitant use of other medications. These limitations preclude establishing a reliable estimate of the risk of adverse fetal and neonatal outcomes with maternal NSAID use. Because the published safety data on neonatal outcomes involved mostly preterm infants, the generalizability of certain reported risks to the full-term infant exposed to NSAIDs through maternal use is uncertain.

Animal Data

Animal reproduction studies have not been conducted with the combination of butalbital, aspirin, caffeine, and codeine phosphate capsules or with butalbital alone.

Codeine:

In a study in which pregnant hamsters were administered 150 mg/kg twice daily of codeine (oral; approximately 14 times the maximum recommended daily dose of 180 mg/day for adults on a mg/m^2 basis) during organogenesis cranial malformations (i.e., meningoencephalocele) in several fetuses were reported; as well as the observation of increases in the percentage of resorptions per litter. Doses of 50 and 150 mg/kg, bid resulted in fetotoxicity as demonstrated by decreased fetal body weight. In an earlier study in hamsters, single oral doses of 73 to 360 mg/kg level on Gestation Day 8 (oral; approximately 4 to 16 times the maximum recommended daily dose of 180 mg/day for adults on a mg/m^2 basis), reportedly produced cranioschisis in all of the fetuses examined.

In studies in rats, doses at the 120 mg/kg level (oral; approximately 6 times the maximum recommended daily dose of 180 mg/day for adults on a mg/m^2 basis) during organogenesis, in the toxic range for the adult animal, were associated with an increase in embryo resorption at the time of implantation.

In pregnant mice, a single 100 mg/kg dose (subcutaneous; approximately 2.8 times the recommended daily dose of 180 mg/day for adults on a mg/mg^2 basis) administered between Gestation Day 7 and 12 reportedly resulted in delayed ossification in the offspring.

No teratogenic effects were observed in rabbits administered up to 30 mg/kg (approximately 4 times the maximum recommended daily dose of 180 mg/day for adults on a mg/m^2 basis) of codeine during organogenesis.

Codeine (30 mg/kg) administered subcutaneously to pregnant rats during pregnancy and for 25 days after delivery increased neonatal mortality at birth. This dose is 1.6 times the maximum recommended human dose of 180 mg/day on a body surface area comparison.

Caffeine:

In studies performed in adult animals, caffeine (as caffeine base) administered to pregnant mice as sustained release pellets at 50 mg/kg (less than the maximum recommended daily dose on a mg/m^2 basis), during the period of organogenesis, caused a low incidence of cleft palate and exencephaly in the fetuses.

8.2 Lactation

Risk Summary

Codeine and its active metabolite, morphine, are present in human milk. There are published studies and cases that have reported excessive sedation, respiratory depression, and death in infants exposed to codeine via breast milk. Women who are ultra-rapid metabolizers of codeine achieve higher than expected serum levels of morphine, potentially leading to higher levels of morphine in breast milk that can be dangerous in their breastfed infants. In women with normal codeine metabolism (normal CYP2D6 activity), the amount of codeine secreted into human milk is low and dose-dependent.

There is no information on the effects of the codeine on milk production. Because of the potential for serious adverse reactions, including excess sedation, respiratory depression, and death in a breastfed infant, advise patients that breastfeeding is not recommended during treatment with BUTALBITAL, ASPIRIN, CAFFEINE and CODEINE PHOSPHATE (see Warnings and Precautions, (5.7)).

The aspirin and caffeine in BUTALBITAL, ASPIRIN, CAFFEINE and CODEINE PHOSPHATE, are also excreted in breast milk in small amounts.

Adverse effects on platelet function in the nursing infant exposed to aspirin in breast milk may be a potential risk. Furthermore, nursing women are advised against aspirin use because of the possible development of Reye's Syndrome in their babies.

Barbiturates and caffeine are also excreted in breast milk in small amounts. Because of potential for serious adverse reactions in nursing infants from Butalbital, aspirin, caffeine, and codeine phosphate capsules, a decision should be made whether to discontinue nursing or to discontinue the drug, taking into account the importance of the drug to the mother.

Clinical Considerations

If infants are exposed to BUTALBITAL, ASPIRIN, CAFFEINE and CODEINE PHOSPHATE, through breast milk, they should be monitored for excess sedation and respiratory depression. Withdrawal symptoms can occur in breastfed infants when maternal administration of an opioid analgesic is stopped, or when breast-feeding is stopped.

8.3 Females and Males of Reproductive Potential

Infertility

Use of opioids for an extended period of time may cause reduced fertility in females and males of reproductive potential. It is not known whether these effects on fertility are reversible [see Adverse Reactions (6.2), Clinical Pharmacology (12.2)], Nonclinical Toxicology (13.1)].

Females

Based on the mechanism of action, the use of prostaglandin-mediated NSAIDs, including aspirin, may delay or prevent rupture of ovarian follicles, which has been associated with reversible infertility in some women. Published animal studies have shown that administration of prostaglandin synthesis inhibitors has the potential to disrupt prostaglandin-mediated follicular rupture required for ovulation. Small studies in women treated with NSAIDs have also shown a reversible delay in ovulation. Consider withdrawal of NSAIDs, including aspirin, in women who have difficulties conceiving or who are undergoing investigation of infertility.

8.4 Pediatric Use

Preparations containing aspirin should be kept out of the reach of children. Reye's Syndrome is a rare condition that affects the brain and liver and is most often observed in children given aspirin during a viral illness. Safety and effectiveness in pediatric patients have not been established.

The safety and effectiveness of BUTALBITAL, ASPIRIN, CAFFEINE and CODEINE PHOSPHATE in pediatric patients have not been established.

Life-threatening respiratory depression and death have occurred in children who received codeine [see Warnings and Precautions (5.6)]. In most of the reported cases, these events followed tonsillectomy and/or adenoidectomy, and many of the children had evidence of being ultra-rapid metabolizers of codeine (i.e., multiple copies of the gene for cytochrome P450 isoenzyme 2D6 or high morphine concentrations). Children with sleep apnea may be particularly sensitive to the respiratory depressant effects of codeine. Because of the risk of life-threatening respiratory depression and death:

- BUTALBITAL, ASPIRIN, CAFFEINE and CODEINE PHOSPHATE is contraindicated for all children younger than 12 years of age [see Contraindications (4)].
- BUTALBITAL, ASPIRIN, CAFFEINE and CODEINE PHOSPHATE is contraindicated for post-operative management in pediatric patients younger than 18 years of age following tonsillectomy and/or adenoidectomy [see Contraindications (4)].
- Avoid the use of BUTALBITAL, ASPIRIN, CAFFEINE and CODEINE PHOSPHATE in adolescents 12 to 18 years of age who have other risk factors that may increase their sensitivity to the respiratory depressant effects of codeine unless the benefits outweigh the risks. Risk factors include conditions associated with hypoventilation, such as postoperative status, obstructive sleep apnea, obesity, severe pulmonary disease, neuromuscular disease, and concomitant use of other medications that cause respiratory depression. [see Warnings and Precautions (5.6)].

8.5 Geriatric Use

Clinical studies of BUTALBITAL, ASPIRIN, CAFFEINE and CODEINE PHOSPHATE did not include sufficient numbers of subjects aged 65 and over to determine whether they respond differently from younger subjects. Other reported clinical experience has not identified differences in responses between the elderly and younger patients. In general, dose selection for an elderly patient should be cautious, usually starting at the low end of the dosing range, reflecting the greater frequency of decreased hepatic, renal, or cardiac function, and of concomitant disease or other drug therapy.

Butalbital is known to be substantially excreted by the kidney, and the risk of toxic reactions to this drug may be greater in patients with impaired renal function. Because elderly patients are more likely to have decreased renal function, care should be taken in dose selection, and it may be useful to regularly evaluate renal function.

Elderly patients (aged 65 years or older) may have increased sensitivity to BUTALBITAL, ASPIRIN, CAFFEINE and CODEINE PHOSPHATE. In general, use caution when selecting a dosage for an elderly patient, usually starting at the low end of the dosing range, reflecting the greater frequency of decreased hepatic, renal, or cardiac function and of concomitant disease or other drug therapy.

Respiratory depression is the chief risk for elderly patients treated with opioids, and has occurred after large initial doses were administered to patients who were not opioid-tolerant or when opioids were co-administered with other agents that depress respiration. Titrate the dosage of BUTALBITAL, ASPIRIN, CAFFEINE and CODEINE PHOSPHATE slowly in geriatric patients and frequently reevaluate the patient for signs of central nervous system and respiratory depression [see Warnings and Precautions (5.9)].

Components of this product are known to be substantially excreted by the kidney, and the risk of adverse reactions to this drug may be greater in patients with impaired renal function. Because elderly patients are more likely to have decreased renal function, care should be taken in dose selection, and it may be useful to monitor renal function.

Elderly patients, compared to younger patients, are at greater risk for NSAID-associated serious cardiovascular, gastrointestinal, and/or renal adverse reactions. If the anticipated benefit for the elderly patient outweighs these potential risks, dose selection should start at the low end of the dosing range, and monitor patients for adverse effects [see Warnings and Precautions(5)].

8.6 Hepatic Impairment

No formal studies have been conducted in patients with hepatic impairment so the pharmacokinetics of aspirin, codeine and butalbital in this patient population are unknown. Start these patients cautiously with lower doses of BUTALBITAL, ASPIRIN, CAFFEINE and CODEINE PHOSPHATE or with longer dosing intervals and titrate slowly while carefully monitoring for side effects. In patients with severe hepatic disease, monitor effects of therapy with serial liver function tests.

8.7 Renal Impairment

BUTALBITAL, ASPIRIN, CAFFEINE and CODEINE PHOSPHATE contains aspirin, which should be avoided in patients with severe renal failure (glomerular filtration rate less than 10 mL/minute).

Codeine pharmacokinetics may be altered in patients with renal failure. Clearance may be decreased and the metabolites may accumulate to much higher plasma levels in patients with renal failure as compared to patients with normal renal function. Start these patients cautiously with lower doses of BUTALBITAL, ASPIRIN, CAFFEINE and CODEINE PHOSPHATE or with longer dosing intervals and titrate slowly while carefully monitoring for side effects. In patients with renal disease, monitor effects of therapy with serial renal function tests.

9 DRUG ABUSE AND DEPENDENCE

9.1 Controlled Substance

BUTALBITAL, ASPIRIN, CAFFEINE and CODEINE PHOSPHATE contains codeine. Codeine in combination with butalbital, aspirin, and caffeine is a Schedule III controlled substance.

9.2 Abuse

BUTALBITAL, ASPIRIN, CAFFEINE and CODEINE PHOSPHATE contains aspirin, butalbital, caffeine, and codeine phosphate, a substance with high potential for misuse and abuse, which can lead to the development of substance use disorder, including addiction [see Warnings and Precautions (5.1)].

Misuse is the intentional use, for therapeutic purposes, of a drug by an individual in a way other than prescribed by a healthcare provider or for whom it was not prescribed.

Abuse is the intentional, non-therapeutic use of a drug, even once, for its desirable psychological or physiological effects.

Drug addiction is a cluster of behavioral, cognitive, and physiological phenomena that may include a strong desire to take the drug, difficulties in controlling drug use (e.g., continuing drug use despite harmful consequences, giving a higher priority to drug use than other activities and obligations), and possible tolerance or physical dependence.

Misuse and abuse of BUTALBITAL, ASPIRIN, CAFFEINE and CODEINE PHOSPHATE increases risk of overdose, which may lead to central nervous system and respiratory depression, hypotension, seizures, and death. The risk is increased with concurrent abuse of BUTALBITAL, ASPIRIN, CAFFEINE and CODEINE PHOSPHATE with alcohol and other CNS depressants. Abuse of and addiction to opioids in some individuals may not be accompanied by concurrent tolerance and symptoms of physical dependence. In addition, abuse of opioids can occur in the absence of addiction.

All patients treated with opioids require careful and frequent reevaluation for signs of misuse, abuse, and addiction, because use of opioid analgesic products carries the risk of addiction even under appropriate medical use. Patients at high risk of BUTALBITAL, ASPIRIN, CAFFEINE and CODEINE PHOSPHATE abuse include those with a history of prolonged use of any opioid, including products containing aspirin, butalbital, caffeine, and codeine phosphate, those with a history of drug or alcohol abuse, or those who use BUTALBITAL, ASPIRIN, CAFFEINE and CODEINE PHOSPHATE in combination with other abused drugs.

“Drug-seeking” behavior is very common in persons with substance use disorders. Drug-seeking tactics include emergency calls or visits near the end of office hours, refusal to undergo appropriate examination, testing, or referral, repeated “loss” of prescriptions, tampering with prescriptions, and reluctance to provide prior medical records or contact information for other treating healthcare provider(s). “Doctor shopping” (visiting multiple prescribers to obtain additional prescriptions) is common among people who abuse drugs and people with substance use disorder. Preoccupation with achieving adequate pain relief can be appropriate behavior in a patient with inadequate pain control.

BUTALBITAL, ASPIRIN, CAFFEINE and CODEINE PHOSPHATE, like other opioids, can be diverted for nonmedical use into illicit channels of distribution. Careful record-keeping of prescribing information, including quantity, frequency, and renewal requests, as required by state and federal law, is strongly advised.

Proper assessment of the patient, proper prescribing practices, periodic reevaluation of therapy, and proper dispensing and storage are appropriate measures that help to limit abuse of opioid drugs.

Risks Specific to Abuse of BUTALBITAL, ASPIRIN, CAFFEINE and CODEINE PHOSPHATE

Abuse of BUTALBITAL, ASPIRIN, CAFFEINE and CODEINE PHOSPHATE poses a risk of overdose and death. The risk is increased with concurrent use of BUTALBITAL, ASPIRIN, CAFFEINE and CODEINE PHOSPHATE with alcohol and/or other CNS depressants.

BUTALBITAL, ASPIRIN, CAFFEINE and CODEINE PHOSPHATE is approved for oral use only.

Parenteral drug abuse is commonly associated with transmission of infectious diseases such as hepatitis and HIV.

Butalbital

Barbiturates may be habit-forming. Tolerance, psychological dependence, and physical dependence may occur especially following prolonged use of high doses of barbiturates. The average daily dose for the barbiturate addict is usually about 1,500 mg. As tolerance to barbiturates develops, the amount needed to maintain the same level of intoxication increases; tolerance to a fatal dosage, however, does not increase more than twofold. As this occurs, the margin between an intoxication dosage and fatal dosage becomes smaller. The lethal dose of a barbiturate is far less if alcohol is also ingested. Major withdrawal symptoms (convulsions and delirium) may occur within 16 hours and last up to 5 days after abrupt cessation of these drugs. Intensity of withdrawal symptoms gradually declines over a period of approximately 15 days. Treatment of barbiturate dependence consists of cautious and gradual withdrawal of the drug. Barbiturate-dependent patients can be withdrawn by using a number of different withdrawal regimens. One method involves initiating treatment at the patient's regular dosage level and gradually decreasing the daily dosage as tolerated by the patient.

9.3 Dependence

Both tolerance and physical dependence can develop during use of opioid therapy.

Tolerance is a physiological state characterized by a reduced response to a drug after repeated administration (i.e., a higher dose of a drug is required to produce the same effect that was once obtained at a lower dose).

Physical dependence is a state that develops as a result of a physiological adaptation in response to repeated drug use, manifested by withdrawal signs and symptoms after abrupt discontinuation or a significant dose reduction of a drug.

Withdrawal may be precipitated through the administration of drugs with opioid antagonist activity (e.g., naloxone, nalmefene), mixed agonist/antagonist analgesics (e.g., pentazocine, butorphanol, nalbuphine), or partial agonists (e.g., buprenorphine). Physical dependence may not occur to a clinically significant degree until after several days to weeks of continued use.

Do not rapidly reduce or abruptly discontinue BUTALBITAL, ASPIRIN, CAFFEINE and CODEINE PHOSPHATE in a patient physically dependent on opioids. Rapid tapering of BUTALBITAL, ASPIRIN, CAFFEINE and CODEINE PHOSPHATE in a patient physically dependent on opioids may lead to serious withdrawal symptoms, uncontrolled pain, and suicide. Rapid discontinuation has also been associated with attempts to find other sources of opioid analgesics, which may be confused with drug-seeking for abuse.

When discontinuing BUTALBITAL, ASPIRIN, CAFFEINE and CODEINE PHOSPHATE, gradually taper the dosage using a patient-specific plan that considers the following: the dose of BUTALBITAL, ASPIRIN, CAFFEINE and CODEINE PHOSPHATE the patient has been taking, the duration of treatment, and the physical and psychological attributes of the patient. To improve the likelihood of a successful taper and minimize withdrawal symptoms, it is important that the opioid tapering schedule is agreed upon by the patient. In patients taking opioids for an extended period of time at high doses, ensure that a multimodal approach to pain management, including mental health support (if needed), is in place prior to initiating an opioid analgesic taper [see Dosage and Administration (2.4), Warnings and Precautions (5.16)].

Infants born to mothers physically dependent on opioids will also be physically dependent and may exhibit respiratory difficulties and withdrawal signs [see Use in Specific Populations (8.1, 8.2)].

10 OVERDOSAGE

Clinical Presentation

Acute overdose with BUTALBITAL, ASPIRIN, CAFFEINE and CODEINE PHOSPHATE can be manifested by respiratory depression, somnolence progressing to stupor or coma, skeletal muscle flaccidity, cold and clammy skin, constricted pupils, and, in some cases, pulmonary edema, bradycardia, hypotension, hypoglycemia, partial or complete airway obstruction, atypical snoring, and death. Marked mydriasis rather than miosis may be seen with hypoxia in overdose situations [see Clinical Pharmacology (12.2)]. Toxic leukoencephalopathy has been reported after opioid overdose and can present hours, days, or weeks after apparent recovery from the initial intoxication.

Signs and Symptoms

Acute Barbiturate Poisoning:

Symptoms include drowsiness, confusion, and coma; respiratory depression; hypotension; hypovolemic shock.

Acute Aspirin Poisoning:

Symptoms include hyperpnea; acid-base disturbances with development of metabolic acidosis; vomiting and abdominal pain; tinnitus, hyperthermia; hypoprothrombinemia; restlessness; delirium; convulsions.

Acute Caffeine Poisoning:

Symptoms include insomnia, restlessness, tremor, and delirium; tachycardia and extrasystoles.

Codeine:

Acute overdose with codeine can be manifested by respiratory depression, somnolence progressing to stupor or coma, skeletal muscle flaccidity, cold and clammy skin, constricted pupils, and, in some cases, pulmonary edema, bradycardia, hypotension, partial or complete airway obstruction, atypical snoring, and death. Marked mydriasis rather than miosis may be seen with hypoxia in overdose situations [see Clinical Pharmacology (12.2)].

Treatment of Overdose

In case of overdose, priorities are the reestablishment of a patent and protected airway and institution of assisted or controlled ventilation, if needed. Employ other supportive measures (including oxygen and vasopressors) in the management of circulatory shock and pulmonary edema as indicated. Cardiac arrest or arrhythmias will require advanced life-support measures.

For clinically significant respiratory or circulatory depression secondary to codeine phosphate overdose, administer an opioid overdose reversal agent such as naloxone or nalmefene.

Because the duration of opioid reversal is expected to be less than the duration of action of codeine in BUTALBITAL, ASPIRIN, CAFFEINE and CODEINE PHOSPHATE, carefully monitor the patient until spontaneous respiration is reliably re-established. If the response to an opioid overdose reversal agentis suboptimal or only brief in nature, administer additional reversal agent as directed by the product's prescribing information.

In an individual physically dependent on opioids, administration of the recommended dosage of the opioid overdose reversal agent will precipitate an acute withdrawal syndrome. The severity of the withdrawal symptoms experienced will depend on the degree of physical dependence and the dose of the reversal agent administered. If a decision is made to treat serious respiratory depression in the physically dependent patient, administration of the reversal agent should be begun with care and by titration with smaller than usual doses of the reversal agent..

Treatment consists primarily of management of barbiturate intoxication, reversal of the effects of codeine, and the correction of the acid-base imbalance due to salicylism. Vomiting should be induced mechanically or with emetics in the conscious patient. Gastric lavage may be used if the pharyngeal and laryngeal reflexes are present and if less than 4 hours have elapsed since ingestion. A cuffed endotracheal tube should be inserted before gastric lavage of the unconscious patient and when necessary to provide assisted respiration. Diuresis, alkalinization of the urine, and correction of electrolyte disturbances should be accomplished through administration of intravenous fluids such as1% sodium bicarbonate and 5% dextrose in water.

Meticulous attention should be given to maintaining adequate pulmonary ventilation. The value of vasopressor agents such as Norepinephrine or Phenylephrine Hydrochloride in treating hypotension is questionable since they increase vasoconstriction and decrease blood flow. However, if prolonged support of blood pressure is required, Norepinephrine Bitartrate (Levophed®) may be given I.V. with the usual precautions and serial blood pressure monitoring. In severe cases of intoxication, peritoneal dialysis, hemodialysis, or exchange transfusion may be lifesaving. Hypoprothrombinemia should be treated with vitamin K, intravenously.

Methemoglobinemia over 30% should be treated with methylene blue by slow intravenous administration.

Naloxone, a narcotic antagonist, can reverse respiratory depression and coma associated with opioid overdose. Typically, a dose of 0.4 to 2 mg is given parenterally and may be repeated if an adequate response is not achieved. Since the duration of action of codeine may exceed that of the antagonist, the patient should be kept under continued surveillance and repeated doses of the antagonist should be administered as needed to maintain adequate respiration. A narcotic antagonist should not be administered in the absence of clinically significant respiratory or cardiovascular depression.

11 DESCRIPTION

BUTALBITAL, ASPIRIN, CAFFEINE and CODEINE PHOSPHATE USP is supplied in capsule form for oral administration.

Each capsule contains the following active ingredients:

Butalbital, USP……………..50 mg

Aspirin, USP………………..325 mg

Caffeine, USP………………40 mg

Codeine phosphate, USP…...30 mg

Butalbital (5-allyl-5-isobutyl-barbituric acid) is a short- to intermediate-acting barbiturate. It has the following structural formula:

Its molecular weight is 224.26 and its molecular formula is C11H16N2O3.

Aspirin (benzoic acid, 2-(acetyloxy)-) is a nonsteroidal anti-inflammatory drug. It has the following structural formula:

Its molecular weight is 180.16 and its molecular formula is C9H8O4.

Caffeine (1,3,7-trimethylxanthine), a methylxanthine, is a central nervous system stimulant. It has the following structural formula:

Its molecular weight is 194.19 and its molecular formula is C8H10N4O2.

Codeine phosphate (7,8-Didehydro-4,5α-epoxy-3-methoxy-17-methylmorphinan-6α-ol phosphate (1:1) (salt) hemihydrate) is an opioid agonist. It has the following structural formula:

Its molecular weight is 397.37 and its molecular formula is C18H24NO7P.

Inactive Ingredients: D&C Yellow #10, D&C Yellow #10 Aluminum Lake, D&C Red #33, D&C Red #28, FD&C Blue #1, FD&C Blue #1 Aluminum Lake, gelatin, microcrystalline cellulose, pregelatinized starch, talc, titanium dioxide, stearic acid, colloidal silicon dioxide.

12 CLINICAL PHARMACOLOGY

12.1 Mechanism of Action

Butalbital, a barbiturate, is a GABAA receptor agonist and may inhibit excitatory AMPA receptors.

Aspirin is a nonsteroidal anti-inflammatory drug and a non-selective irreversible inhibitor of cyclooxygenases.

Caffeine is a methylxanthine and CNS stimulant. The exact mechanism with respect to the indication is not clear; however, the effects of caffeine may be due to antagonism of adenosine receptors.

Codeine is an opioid agonist relatively selective for the mu-opioid receptor, but with a much weaker affinity than morphine. The analgesic properties of codeine have been speculated to come from its conversion to morphine, although the exact mechanism of analgesic action remains unknown.

12.2 Pharmacodynamics

Effects on the Central Nervous System

Butalbital, a barbiturate, is a central nervous system (CNS) depressant that can produce sedation, respiratory depression, and euphoria. The potential impact of butalbital on painful stimuli is not clear and in some individuals barbiturates may increase reaction to painful stimuli.

Codeine produces respiratory depression by direct action on brain stem respiratory centers. The respiratory depression involves a reduction in the responsiveness of the brain stem respiratory centers to both increases in carbon dioxide tension and electrical stimulation.

Codeine causes miosis, even in total darkness. Pinpoint pupils are a sign of opioid overdose but are not pathognomonic (e.g., pontine lesions of hemorrhagic or ischemic origins may produce similar findings). Marked mydriasis rather than miosis may be seen due to hypoxia in overdose situations.

Aspirin works by inhibiting the body's production of prostaglandins, including prostaglandins involved in inflammation. Prostaglandins cause pain sensations by stimulating muscle contractions and dilating blood vessels throughout the body. In the CNS, aspirin works on the hypothalamus heat-regulating center to reduce fever, however, other mechanisms may be involved.

Effects on the Gastrointestinal Tract and Other Smooth Muscle

Codeine causes a reduction in motility associated with an increase in smooth muscle tone in the antrum of the stomach and duodenum. Digestion of food in the small intestine is delayed and propulsive contractions are decreased. Propulsive peristaltic waves in the colon are decreased, while tone may be increased to the point of spasm, resulting in constipation. Other opioid-induced effects may include a reduction in biliary and pancreatic secretions, spasm of sphincter of Oddi, transient elevations in serum amylase, and opioid-induced esophageal dysfunction (OIED).

Aspirin can produce gastrointestinal injury (lesions, ulcers) through a mechanism that is not yet completely understood, but may involve a reduction in eicosanoid synthesis by the gastric mucosa. Decreased production of prostaglandins may compromise the defenses of the gastric mucosa and the activity of substances involved in tissue repair and ulcer healing.

Effects on the Cardiovascular System

Butalbital may decrease blood pressure and heart rate when administered at sedative and hypnotic doses.

Codeine produces peripheral vasodilation which may result in orthostatic hypotension or syncope. Manifestations of histamine release and/or peripheral vasodilation may include pruritus, flushing, red eyes, sweating. and/or orthostatic hypotension.

Aspirin affects platelet aggregation by irreversibly inhibiting prostaglandin cyclooxygenase. This effect lasts for the life of the platelet and prevents the formation of the platelet aggregating factor, thromboxane A2. Nonacetylated salicylates do not inhibit this enzyme and have no effect on platelet aggregation. At somewhat higher doses, aspirin reversibly inhibits the formation of prostaglandin 12 (prostacyclin), which is an arterial vasodilator and inhibits platelet aggregation.

Effects on the Endocrine System

Opioids inhibit the secretion of adrenocorticotropic hormone (ACTH), cortisol, and luteinizing hormone (LH) in humans [see Adverse Reactions (6.2)]. They also stimulate prolactin, growth hormone (GH) secretion, and pancreatic secretion of insulin and glucagon.

Use of opioids for an extended period of time may influence the hypothalamic-pituitary-gonadal axis, leading to androgen deficiency that may manifest as low libido, impotence, erectile dysfunction, amenorrhea, or infertility. The causal role of opioids in the clinical syndrome of hypogonadism is unknown because the various medical, physical, lifestyle, and psychological stressors that may influence gonadal hormone levels have not been adequately controlled for in studies conducted to date [see Adverse Reactions (6.2)].

Effects on the Immune System

Opioids have been shown to have a variety of effects on components of the immune system in in vitro and animal models. The clinical significance of these findings is unknown. Overall, the effects of opioids appear to be modestly immunosuppressive.

Concentration–Efficacy Relationships

The minimum effective analgesic concentration will vary widely among patients, especially among patients who have been previously treated with opioid agonist . The minimum effective analgesic concentration of codeine for any individual patient may increase over time due to an increase in pain, the development of a new pain syndrome and/or the development of analgesic tolerance [see Dosage and Administration (2.1, 2.3)].

Concentration–Adverse Reaction Relationships

There is a relationship between increasing codeine plasma concentration and increasing frequency of dose-related opioid adverse reactions such as nausea, vomiting, CNS effects, and respiratory depression. In opioid-tolerant patients, the situation may be altered by the development of tolerance to opioid-related adverse reactions [see Dosage and Administration (2.1, 2.3, 0)].

12.3 Pharmacokinetics

Bioavailability:

The bioavailability of the components of the fixed combination of BUTALBITAL, ASPIRIN, CAFFEINE and CODEINE PHOSPHATE is identical to their bioavailability when butalbital, aspirin, caffeine and codeine phosphate are administered separately in equivalent molar doses. The behavior of the individual components is described below.

Aspirin

Absorption

The systemic availability of aspirin after an oral dose is highly dependent on the dosage form, the presence of food, the gastric emptying time, gastric pH, antacids, buffering agents, and particle size. These factors affect not necessarily the extent of absorption of total salicylates but more the stability of aspirin prior to absorption.

Distribution

During the absorption process and after absorption, aspirin is mainly hydrolyzed to salicylic acid and distributed to all body tissues and fluids, including fetal tissues, breast milk, and the central nervous system (CNS). Highest concentrations are found in plasma, liver, renal cortex, heart, and lung. In plasma, about 50%-80% of the salicylic acid and its metabolites are loosely bound to plasma proteins.

Elimination

Metabolism

The biotransformation of aspirin occurs primarily in the hepatocytes. The major metabolites are salicyluric acid (75%), the phenolic and acyl glucuronides of salicylate (15%), and gentisic and gentisuric acid (1%). The bioavailability of the aspirin component of BUTALBITAL, ASPIRIN, CAFFEINE and CODEINE PHOSPHATE is equivalent to that of a solution except for a slower rate of absorption. A peak concentration of 8.8 mcg/mL was obtained at 40 minutes after a 650 mg dose.

Excretion

The clearance of total salicylates is subject to saturable kinetics; however, first-order elimination kinetics are still a good approximation for doses up to 650 mg. The plasma half-life for aspirin is about 12 minutes and for salicylic acid and/or total salicylates is about 3 hours.

The elimination of therapeutic doses is through the kidneys either as salicylic acid or other biotransformation products. The renal clearance is greatly augmented by an alkaline urine as is produced by concurrent administration of sodium bicarbonate or potassium citrate.

Codeine

Absorption

Codeine is readily absorbed from the gastrointestinal tract. The bioavailability of the codeine component of BUTALBITAL, ASPIRIN, CAFFEINE and CODEINE PHOSPHATE is equivalent to that of a solution. Peak concentrations of 198 ng/mL were obtained at 1 hour after a 60 mg dose. At therapeutic doses, the analgesic effect reaches a peak within 2 hours and persists between 4 and 6 hours.

Distribution

It is rapidly distributed from the intravascular spaces to the various body tissues, with preferential uptake by parenchymatous organs such as the liver, spleen, and kidney. Codeine crosses the blood-brain barrier, and is found in fetal tissue and breast milk. The plasma concentration does not correlate with brain concentration or relief of pain, however, codeine is not bound to plasma proteins and does not accumulate in body tissues.

Elimination

Metabolism

About 70-80% of administered dose of codeine is metabolized by conjugation with glucuronic acid to codeine6glucuronide (C6G) and via O-demethylation to morphine (about 5-10%) and N-demethylation to norcodeine (about 10%) respectively. UDP-glucuronosyltransferase (UGT) 2B7 and 2B4 are the major enzymes mediating glucurodination of codeine to C6G. Cytochrome P450 2D6 is the major enzyme responsible for conversion of codeine to morphine and P450 3A4 is the major enzyme mediating conversion of codeine to norcodeine. Morphine and norcodeine are further metabolized by conjugation with glucuronic acid. The glucuronide metabolites of morphine are morphine-3-glucuronide (M3G) and morphine-6-glucuronide (M6G). Morphine and M6G are known to have analgesic activity in humans. The analgesic activity of C6G in humans is unknown. Norcodeine and M3G are generally not considered to possess analgesic properties.

Excretion

The plasma half-life is about 2.9 hours. The elimination of codeine is primarily via the kidneys, and about 90% of an oral dose is excreted by the kidneys within 24 hours of dosing. The urinary secretion products consist of free and glucuronide-conjugated codeine (about 70%), free and conjugated norcodeine (about 10%), free and conjugated morphine (about 10%), normorphine (4%), and hydrocodone (1%). The remainder of the dose is excreted in the feces.

Butalbital

Absorption

Butalbital is well absorbed from the gastrointestinal tract. The bioavailability of the butalbital component of BUTALBITAL, ASPIRIN, CAFFEINE and CODEINE PHOSPHATE is equivalent to that of a solution except for a decrease in the rate of absorption. A peak concentration of 2,020 ng/mL is obtained at about 1.5 hours after a 100 mg dose.

Distribution

Butalbital is expected to distribute to most of the tissues in the body. Barbiturates, in general, may appear in breast milk and readily cross the placental barrier. They are bound to plasma and tissue proteins to a varying degree and binding increases directly as a function of lipid solubility.

The in vitro plasma protein binding of butalbital is 45% over the concentration range of 0.5 to 20 mcg/mL. This falls within the range of plasma protein binding (20% to 45%) reported with other barbiturates such as phenobarbital, pentobarbital, and secobarbital sodium. The plasma-to-blood concentration ratio was almost unity indicating that there is no preferential distribution of butalbital into either plasma or blood cells.

Elimination

Elimination of butalbital is primarily via the kidney (59% to 88% of the dose) as unchanged drug or metabolites. The plasma half-life is about 35 hours. Urinary excretion products included parent drug (about 3.6% of the dose), 5-isobutyl-5-(2,3-dihydroxypropyl) barbituric acid (about 24% of the dose), 5-allyl-5(3-hydroxy-2-methyl-1-propyl) barbituric acid (about 4.8% of the dose), products with the barbituric acid ring hydrolyzed with excretion of urea (about 14% of the dose), as well as unidentified materials. Of the material excreted in the urine, 32% was conjugated.

Caffeine

Absorption

Like most xanthines, caffeine is rapidly absorbed and distributed in all body tissues and fluids, including the CNS, fetal tissues, and breast milk. The bioavailability of the caffeine component for BUTALBITAL, ASPIRIN, CAFFEINE and CODEINE PHOSPHATE is equivalent to that of a solution except for a slightly longer time to peak. A peak concentration of 1,660 ng/mL was obtained in less than an hour for an 80 mg dose.

Distribution

Caffeine is distributed in all body tissues and fluids, including the CNS, fetal tissues, and breast milk.

Elimination

Caffeine is cleared rapidly through metabolism and excretion in the urine.

Metabolism

Caffeine is mainly metabolized by CYP1A2. Other enzymes, including CYP2E1, CYP3A4, CYP2C8 and CYP2C9 may play a minor role in its metabolism. Hepatic biotransformation prior to excretion results in about equal amounts of 1-methylxanthine and 1-methyluric acid.

Excretion

Of the 70% of the dose that has been recovered in the urine, only 3% was unchanged drug. The plasma half-life is about 3 hours.

13 NONCLINICAL TOXICOLOGY

13.1 Carcinogenesis, Mutagenesis, Impairment of Fertility

Carcinogenesis

Long-term studies in animals to evaluate the carcinogenic potential of the combination of butalbital, aspirin, caffeine, and codeine or butalbital alone have not been conducted.

Administration of aspirin for 68 weeks at 0.5 percent in the feed of rats was not carcinogenic.

Two-year carcinogenicity studies with codeine sulfate have been conducted in F344/N rats and B6C3F1 mice. There was no evidence of carcinogenicity in male and female rats, respectively, at dietary doses up to 70 and 80 mg/kg/day of codeine sulfate (approximately 4 times the maximum recommended daily dose of 180 mg/day for adults on a mg/m^2 basis) for two years. Similarly there was no evidence of carcinogenicity activity in male and female mice at dietary doses up to 400 mg/kg/day of codeine sulfate (approximately 10 times the maximum recommended daily dose of 180 mg/day for adults on a mg/m^2 basis) for two years.

In a 2-year study in Sprague-Dawley rats, caffeine (as caffeine base) administered in drinking water was not carcinogenic in male rats at doses up to 102 mg/kg or in female rats at doses up to 170 mg/kg (approximately 4 and 7 times, respectively, the maximum human daily dose on a mg/m^2 basis). In an 18-month study in C57BL/6 mice, no evidence of tumorigenicity was seen at dietary doses up to 55 mg/kg (equivalent to the MHDD on a mg/m^2 basis).

Mutagenesis

There are no genetic toxicology data for butalbital.

Codeine sulfate was not mutagenic in the in vitro bacterial reverse mutation assay or clastogenic in the in vitro Chinese hamster ovary cell chromosome aberration assay.

Aspirin is not mutagenic in the Ames Salmonella assay; however, aspirin did induce chromosome aberrations in cultured human fibroblasts.

Caffeine (as caffeine base) increased the sister chromatid exchange (SCE) SCE/cell metaphase (exposure time dependent) in an in vivo mouse metaphase analysis. Caffeine also potentiated the genotoxicity of known mutagens and enhanced the micronuclei formation (5-fold) in folate-deficient mice. However, caffeine did not increase chromosomal aberrations in in vitro Chinese hamster ovary cell (CHO) and human lymphocyte assays and was not mutagenic in an in vitro CHO/hypoxanthine guanine phosphoribosyltransferase (HGPRT) gene mutation assay, except at cytotoxic concentrations. In addition, caffeine was not clastogenic in an in vivo mouse micronucleus assay. Caffeine was negative in the in vitro bacterial reverse mutation assay (Ames test).

Impairment of Fertility

No adequate studies have been conducted in animals to characterize the impact of the combinations of butalbital, aspirin, caffeine, and codeine on fertility. There are also no data on butalbital alone or codeine alone.

Aspirin inhibits ovulation in rats.

Caffeine (as caffeine base) administered to male rats at 50 mg/kg/day subcutaneously (2 times the MHDD on a mg/m^2 basis) for 4 days prior to mating with untreated females, caused decreased male reproductive performance in addition to causing embryotoxicity. In addition, long-term exposure to high oral doses of caffeine (3 g over 7 weeks) was toxic to rat testes as manifested by spermatogenic cell degeneration.

14 CLINICAL TRIALS

Evidence supporting the efficacy of BUTALBITAL, ASPIRIN, CAFFEINE and CODEINE PHOSPHATE is derived from 2 multi-clinic trials that compared patients with tension headache randomly assigned to 4 parallel treatments: BUTALBITAL, ASPIRIN, CAFFEINE and CODEINE PHOSPHATE, codeine, butalbital + aspirin + caffeine capsules, USP, and placebo. Response was assessed over the course of the first 4 hours of each of 2 distinct headaches, separated by at least 24 hours BUTALBITAL, ASPIRIN, CAFFEINE and CODEINE PHOSPHATE proved statistically significantly superior to each of its components and to placebo on measures of pain relief.

Evidence supporting the efficacy and safety of BUTALBITAL, ASPIRIN, CAFFEINE and CODEINE PHOSPHATE in the treatment of multiple recurrent headaches is unavailable. Caution in this regard is required because codeine and butalbital are habit-forming and potentially abusable.

16 HOW SUPPLIED/STORAGE AND HANDLING

Each yellow and blue BUTALBITAL, ASPIRIN, CAFFEINE and CODEINE PHOSPHATE Capsule USP 50 mg/325 mg/ 40 mg/30 mg is imprinted JSP 507

Bottles of 100 NDC 69238-1993-1

Store and Dispense

Below 25°C (77°F); in a tight, light resistant container.

Keep out of reach of children

17 PATIENT COUNSELING INFORMATION

Advise the patient to read the FDA-approved patient labeling (Medication Guide).

Storage and Disposal

Because of the risks associated with accidental ingestion, misuse, and abuse, advise patients to store BUTALBITAL, ASPIRIN, CAFFEINE and CODEINE PHOSPHATE securely, out of sight and reach of children, and in a location not accessible by others, including visitors to the home. Inform patients that leaving BUTALBITAL, ASPIRIN, CAFFEINE and CODEINE PHOSPHATE unsecured can pose a deadly risk to others in the home [see Warnings and Precautions (5.1, 5.5), Drug Abuse and Dependence (9.2)].

Advise patients and caregivers that when medicines are no longer needed, they should be disposed of promptly. Inform patients that medicine take-back options are the preferred way to safely dispose of most types of unneeded medicines. If no take back programs or DEA-registered collectors are available, instruct patients to dispose of BUTALBITAL, ASPIRIN, CAFFEINE and CODEINE PHOSPHATE by following these four steps:

- Mix BUTALBITAL, ASPIRIN, CAFFEINE and CODEINE PHOSPHATE (do not crush) with an unpalatable substance such as dirt, cat litter, or used coffee grounds;
- Place the mixture in a container such as a sealed plastic bag;
- Throw the container in the household trash;
- Delete all personal information on the prescription label of the empty bottle

Inform patients that they can visit www.fda.gov/drugdisposal for additional information on disposal of unused medicines.

Addiction, Abuse, and Misuse

Inform patients that the use of BUTALBITAL, ASPIRIN, CAFFEINE and CODEINE PHOSPHATE, even when taken as recommended, can result in addiction, abuse, and misuse, which can lead to overdose and death [see Warnings and Precautions (5.1)]. Instruct patients not to share BUTALBITAL, ASPIRIN, CAFFEINE and CODEINE PHOSPHATE with others and to take steps to protect BUTALBITAL, ASPIRIN, CAFFEINE and CODEINE PHOSPHATE from theft or misuse.

Life-Threatening Respiratory Depression

Inform patients of the risk of life-threatening respiratory depression, including information that the risk is greatest when starting BUTALBITAL, ASPIRIN, CAFFEINE and CODEINE PHOSPHATE or when the dosage is increased, and that it can occur even at recommended dosages.

Educate patients and caregivers on how to recognize respiratory depression and emphasize the importance of calling 911 or getting emergency medical help right away in the event of a known or suspected overdose [see Warnings and Precautions (5.2)]

Accidental Ingestion

Inform patients that accidental ingestion, especially by children, may result in respiratory depression or death.

Instruct patients to take steps to store BUTALBITAL, ASPIRIN, CAFFEINE and CODEINE PHOSPHATE securely and to properly dispose of unused BUTALBITAL, ASPIRIN, CAFFEINE and CODEINE PHOSPHATE in accordance with the local state guidelines and/or regulations.

Risks from Concomitant Use with Benzodiazepines and Other CNS Depressants

Inform patients and caregivers that potentially fatal additive effects may occur if BUTALBITAL, ASPIRIN, CAFFEINE and CODEINE PHOSPHATE is used with benzodiazepines or other CNS depressants, including alcohol (e.g., non-benzodiazepine sedative/hypnotics, anxiolytics, tranquilizers, muscle relaxants, general anesthetics, antipsychotics, gabapentinoids [gabapentin or pregabalin], and other opioids), and not to use these concomitantly unless supervised by a health care provider [see Warnings and Precautions (5.3), Drug Interactions (7)].

Patient Access to an Opioid Overdose Reversal Agent for the Emergency Treatment of Opioid Overdose

Inform patients and caregivers about opioid overdose reversal agents (e.g., naloxone, nalmefene). Discuss the importance of having access to an opioid overdose reversal agent, especially if the patient has risk factors for overdose (e.g., concomitant use of CNS depressants, a history of opioid use disorder, or prior opioid overdose) or if there are household members (including children) or other close contacts at risk for accidental ingestion or opioid overdose.

Discuss with the patient the options for obtaining an opioid overdose reversal agent (e.g., prescription, over-the-counter, or as part of a community-based program) [see Dosage and Administration (2.2), Warnings and Precautions (5.2)].

Educate patients and caregivers on how to recognize the signs and symptoms of an overdose.

Explain to patients and caregivers that effects of opioid overdose reversal agents like naloxone and nalmefene are temporary, and that they must call 911 or get emergency medical help right away in all cases of known or suspected opioid overdose, even if an opioid overdose reversal agent is administered [see Overdosage (10)].

Advise patients and caregivers:

- how to treat with the overdose reversal agent in the event of an opioid overdose
- to tell family and friends about the opioid overdose reversal agent, and to keep it in a place where family and friends can access it in an emergency
- to read the Patient Information (or other educational material) that will come with their opioid overdose reversal agent. Emphasize the importance of doing this before an opioid emergency happens, so the patient and caregiver will know what to do.

Ultra-Rapid Metabolism of Codeine and Other Risk Factors for Life-threatening Respiratory Depression in Children

Advise caregivers that BUTALBITAL, ASPIRIN, CAFFEINE and CODEINE PHOSPHATE is contraindicated in all children younger than 12 years of age and in children younger than 18 years of age following tonsillectomy and/or adenoidectomy. Advise caregivers of children 12-18 years of age receiving BUTALBITAL, ASPIRIN, CAFFEINE and CODEINE PHOSPHATE to monitor for signs of respiratory depression [see Warnings and Precautions (5.6)].

Hyperalgesia and Allodynia

Inform patients and caregivers not to increase opioid dosage without first consulting a clinician. Advise patients to seek medical attention if they experience symptoms of hyperalgesia, including worsening pain, increased sensitivity to pain, or new pain [see Warnings and Precautions (5.8); Adverse Reactions (6.2)].

Serotonin Syndrome

Inform patients that opioids could cause a rare but potentially life-threatening condition resulting from concomitant administration of serotonergic drugs. Warn patients of the symptoms of serotonin syndrome and to seek medical attention right away if symptoms develop. Instruct patients to inform their healthcare providers if they are taking, or plan to take serotonergic medications. [see Drug Interactions (7)].

MAOI Interaction

Inform patients not to take BUTALBITAL, ASPIRIN, CAFFEINE and CODEINE PHOSPHATE while using any drugs that inhibit monoamine oxidase. Patients should not start MAOIs while taking BUTALBITAL, ASPIRIN, CAFFEINE and CODEINE PHOSPHATE [see Drug Interactions (7)].

Important Administration Instructions

Instruct patients how to properly take BUTALBITAL, ASPIRIN, CAFFEINE and CODEINE PHOSPHATE. [see Dosage and Administration (2.3)]. Patients should take the drug only for as long as it is prescribed, in the amounts prescribed, and no more frequently than prescribed.

Important Discontinuation Instructions

In order to avoid developing withdrawal symptoms, instruct patients not to discontinue BUTALBITAL, ASPIRIN, CAFFEINE and CODEINE without first discussing a tapering plan with the prescriber [see Dosage and Administration (2.4)].

Driving or Operating Heavy Machinery

Inform patients that BUTALBITAL, ASPIRIN, CAFFEINE and CODEINE PHOSPHATE may impair the ability to perform potentially hazardous activities such as driving a car or operating heavy machinery. Advise patients not to perform such tasks until they know how they will react to the medication [see Warnings and Precautions (5.18)].

Risk of Bleeding

Inform patients about the signs and symptoms of bleeding. Tell patients to notify their physician if they are prescribed any drug which may increase risk of bleeding.

Counsel patients who consume three or more alcoholic drinks daily about the bleeding risks involved with chronic, heavy alcohol use while taking aspirin [see Warnings and Precautions (5.19)].

Constipation

Advise patients of the potential for severe constipation, including management instructions and when to seek medical attention [see Adverse Reactions (6)].

Adrenal Insufficiency

Inform patients that opioids could cause adrenal insufficiency, a potentially life-threatening condition. Adrenal insufficiency may present with non-specific symptoms and signs such as nausea, vomiting, anorexia, fatigue, weakness, dizziness, and low blood pressure. Advise patients to seek medical attention if they experience a constellation of these symptoms [see Warnings and Precautions (5.11)].

Hypotension

Inform patients that BUTALBITAL, ASPIRIN, CAFFEINE and CODEINE PHOSPHATE may cause orthostatic hypotension and syncope. Instruct patients how to recognize symptoms of low blood pressure and how to reduce the risk of serious consequences should hypotension occur (e.g., sit or lie down, carefully rise from a sitting or lying position) [see Warnings and Precautions (5.12)].

Anaphylaxis

Inform patients that anaphylaxis has been reported with ingredients contained in BUTALBITAL, ASPIRIN, CAFFEINE and CODEINE PHOSPHATE. Advise patients how to recognize such a reaction and when to seek medical attention [see Contraindications (4), Adverse Reactions (6)].

Aspirin Allergy

Patients should be informed that BUTALBITAL, ASPIRIN, CAFFEINE and CODEINE PHOSPHATE contains aspirin and should not be taken by patients with an aspirin or NSAIDs allergy [see Warnings and Precautions (5.23)].

Pregnancy

Neonatal Opioid Withdrawal Syndrome

Inform female patients of reproductive potential that use of BUTALBITAL, ASPIRIN, CAFFEINE and CODEINE PHOSPHATE for an extended period of time during pregnancy can result in neonatal opioid withdrawal syndrome, which may be life-threatening if not recognized and treated [see Warnings and Precautions (5.4), Use in Specific Populations (8.1)].

Embryo-Fetal Toxicity

Inform female patients of reproductive potential that BUTALBITAL, ASPIRIN, CAFFEINE and CODEINE PHOSPHATE can (or may) cause fetal harm and to inform the healthcare provider of a known or suspected pregnancy. Inform pregnant women to avoid use of aspirin and other NSAIDs starting at 30 weeks gestation because of the risk of the premature closing of the fetal ductus arteriosus. If treatment with BUTALBITAL, ASPIRIN, CAFFEINE and CODEINE PHOSPHATE is needed for a pregnant woman between about 20 to 30 weeks gestation, advise her that she may need to be monitored for oligohydramnios, if treatment continues for longer than 48 hours [see Warnings and Precautions (5.17) and Use in Specific Populations (8.1)].

Lactation

Advise women that breastfeeding is not recommended during treatment with BUTALBITAL,

ASPIRIN, CAFFEINE and CODEINE PHOSPHATE [see Use in Specific Populations (8.2)].

Infertility

Inform patients that use of opioids for an extended period of time may cause reduced fertility. It is not known whether these effects on fertility are reversible [see Use in Specific Populations (8.3)].

Serious Skin Reactions, including DRESS

Advise patients to stop taking BUTALBITAL, ASPIRIN, CAFFEINE and CODEINE PHOSPHATE immediately if they develop any type of rash or fever and to contact their healthcare provider as soon as possible [see Warnings and Precautions (5.21)].

Rx ONLY

Manufactured by:
Jerome Stevens Pharmaceuticals, Inc.
Bohemia, NY 11716

Distributed by:
Amneal Pharmaceuticals LLC
Bridgewater, NJ 08807

Medication Guide
BUTALBITAL, ASPIRIN, CAFFEINE and CODEINE PHOSPHATE capsules

BUTALBITAL, ASPIRIN, CAFFEINE and CODEINE PHOSPHATE is:

- A strong prescription pain medicine that contains an opioid (narcotic) that is indicated for the relief of the symptom complex of tension (or muscle contraction) headache, when other pain treatments such as non-opioid pain medicines do not treat your pain well enough or you cannot tolerate them.
- An opioid pain medicine that can put you at risk for overdose and death. Even if you take your dose correctly as prescribed you are at risk for opioid addiction, abuse, and misuse that can lead to death.

Important information about BUTALBITAL, ASPIRIN, CAFFEINE and CODEINE PHOSPHATE:

- Get emergency help or call 911 right away if you take too much BUTALBITAL, ASPIRIN, CAFFEINE and CODEINE PHOSPHATE (overdose). When you first start taking BUTALBITAL, ASPIRIN, CAFFEINE and CODEINE PHOSPHATE, when your dose is changed, or if you take too much (overdose), serious or life-threatening breathing problems that can lead to death may occur. Ask your healthcare provider about medicines like naloxone, or nalmefene that can be used in an emergency to reverse an opioid overdose.
- Taking BUTALBITAL, ASPIRIN, CAFFEINE and CODEINE PHOSPHATE with other opioid medicines, benzodiazepines, gabapentinoids (gabapentin or pregabalin), alcohol, or other central nervous system depressants (including street drugs) can cause severe drowsiness, decreased awareness, breathing problems, coma, and death.
- Never give anyone else your BUTALBITAL, ASPIRIN, CAFFEINE and CODEINE PHOSPHATE. They could die from taking it. Selling or giving away BUTALBITAL, ASPIRIN, CAFFEINE and CODEINE PHOSPHATE is against the law.
- Store BUTALBITAL, ASPIRIN, CAFFEINE and CODEINE PHOSPHATE securely, out of sight and reach of children, and in a location not accessible by others, including visitors to the home.

Important Information Guiding Use in Pediatric Patients:

- Do not give BUTALBITAL, ASPIRIN, CAFFEINE and CODEINE PHOSPHATE to a child younger than 12 years of age.
- Do not give BUTALBITAL, ASPIRIN, CAFFEINE and CODEINE PHOSPHATE to a child younger than 18 years of age after surgery to remove the tonsils and/or adenoids.
- Avoid giving BUTALBITAL, ASPIRIN, CAFFEINE and CODEINE PHOSPHATE to children between 12 to 18 years of age who have risk factors for breathing problems such as obstructive sleep apnea, obesity, or underlying lung problems.

Do not give BUTALBITAL, ASPIRIN, CAFFEINE and CODEINE PHOSPHATE to a child or teenager with a viral illness. Reye's syndrome, a life-threatening condition, can happen when aspirin (an ingredient in BUTALBITAL, ASPIRIN, CAFFEINE and CODEINE PHOSPHATE) is used in children and teenagers who have certain viral illnesses.
Do not take BUTALBITAL, ASPIRIN, CAFFEINE and CODEINE PHOSPHATE if you have:

- severe asthma, trouble breathing, or other lung problems.
- a bowel blockage or have narrowing of the stomach or intestines.
- known allergy to nonsteroidal anti-inflammatory drug products (NSAIDs)
- a rare disorder in which your blood doesn't clot normally (hemophilia)

Before taking BUTALBITAL, ASPIRIN, CAFFEINE and CODEINE PHOSPHATE, tell your healthcare provider if you have a history of:

- head injury, seizures
- liver, kidney, thyroid problems
- problems urinating
- pancreas or gallbladder problems
- abuse of street or prescription drugs, alcohol addiction, opiod overdose or mental health problems.
- have been told by your healthcare provider that you are a “rapid metabolizer” of certain medicines

Tell your healthcare provider if you:

- notice your pain getting worse. If your pain gets worse after you take BUTALBITAL, ASPIRIN, CAFFEINE and CODEINE PHOSPHATE, do not take more of BUTALBITAL, ASPIRIN, CAFFEINE and CODEINE PHOSPHATE without first talking to your healthcare provider. Talk to your healthcare provider if the pain that you have increases, if you feel more sensitive to pain, or if you have new pain after taking BUTALBITAL, ASPIRIN, CAFFEINE and CODEINE PHOSPHATE.
- are pregnant or planning to become pregnant. BUTALBITAL, ASPIRIN, CAFFEINE and CODEINE PHOSPHATE may harm your baby. Use of BUTALBITAL, ASPIRIN, CAFFEINE and CODEINE PHOSPHATE for an extended period of time during pregnancy can cause withdrawal symptoms in your newborn baby that could be life-threatening if not recognized and treated. Taking NSAID-containing products like BUTALBITAL, ASPIRIN, CAFFEINE and CODEINE PHOSPHATE at about 20 weeks of pregnancy or later may harm your unborn baby. If you need to take NSAIDs for more than 2 days when you are between 20 and 30 weeks of pregnancy, your healthcare provider may need to monitor the amount of fluid in your womb around your baby. You should not take NSAIDs after about 30 weeks of pregnancy.
- breast-feeding. Not recommended; may harm your baby.
- develop any type of rash or fever. Contact your healthcare provider as soon as possible and stop taking BUTALBITAL, ASPIRIN, CAFFEINE and CODEINE PHOSPHATE.
- living in a household where there are small children or someone who has abused street or prescription drugs
- taking prescription or over-the-counter medicines, vitamins, or herbal supplements. Taking BUTALBITAL, ASPIRIN, CAFFEINE and CODEINE PHOSPHATE with certain other medicines can cause serious side effects that could lead to death.

When taking BUTALBITAL, ASPIRIN, CAFFEINE and CODEINE PHOSPHATE:

- Do not change your dose. Take BUTALBITAL, ASPIRIN, CAFFEINE and CODEINE PHOSPHATE exactly as prescribed by your healthcare provider. Use the lowest dose possible for the shortest time needed.
- For acute (short-term) pain, you may only need to take BUTALBITAL, ASPIRIN, CAFFEINE and CODEINE PHOSPHATE for a few days. You may have some BUTALBITAL, ASPIRIN, CAFFEINE and CODEINE PHOSPHATE left over that you did not use. See disposal information at the bottom of this section for directions on how to safely throw away (dispose of) your unused BUTALBITAL, ASPIRIN, CAFFEINE and CODEINE PHOSPHATE.
- Take your prescribed dose of 1 or 2 capsules every 4 hours as needed for pain. Total daily dosage should not exceed 6 capsules. Do not take more than your prescribed dose. If you miss a dose, take your next dose at your usual time.
- Call your healthcare provider if the dose you are taking does not control your pain.
- If you have been taking BUTALBITAL, ASPIRIN, CAFFEINE and CODEINE PHOSPHATE regularly, do not stop taking BUTALBITAL, ASPIRIN, CAFFEINE and CODEINE PHOSPHATE without talking to your healthcare provider. Dispose of expired, unwanted, or unused BUTALBITAL, ASPIRIN, CAFFEINE and CODEINE PHOSPHATE by taking your drug to an authorized DEA- registered collector or drug take-back program. If one is not available, you can dispose of BUTALBITAL, ASPIRIN, CAFFEINE and CODEINE PHOSPHATE by mixing the product with dirt, cat litter, or coffee grounds; placing the mixture in a sealed plastic bag and throwing the bag in your trash. Visit www.fda.gov/drugdisposal for additional information on disposal of unused medicines.

While taking BUTALBITAL, ASPIRIN, CAFFEINE and CODEINE PHOSPHATE DO NOT:

- Drive or operate heavy machinery, until you know how BUTALBITAL, ASPIRIN, CAFFEINE and CODEINE PHOSPHATE affects you. BUTALBITAL, ASPIRIN, CAFFEINE and CODEINE PHOSPHATE can make you sleepy, dizzy, or lightheaded.
- Drink alcohol or use prescription or over-the-counter medicines that contain alcohol. Using products containing alcohol during treatment with BUTALBITAL, ASPIRIN, CAFFEINE and CODEINE PHOSPHATE may cause you to overdose and die.

The possible side effects of BUTALBITAL, ASPIRIN, CAFFEINE and CODEINE PHOSPHATE:

- constipation, nausea, sleepiness, vomiting, tiredness, headache, dizziness, abdominal pain, rash, or fever. Call your healthcare provider if you have any of these symptoms and they are severe.

Get emergency medical help or call 911 right away if you have:

- trouble breathing, shortness of breath, fast heartbeat, chest pain, swelling of your face, tongue, or throat, extreme drowsiness, light-headedness when changing positions, feeling faint, agitation, high body temperature, trouble walking, stiff muscles, or mental changes such as confusion.
- If you are a nursing mother taking BUTALBITAL, ASPIRIN, CAFFEINE and CODEINE PHOSPHATE and your breastfeeding baby has increased sleepiness, confusion, difficulty breathing, shallow breathing, limpness, or difficulty breastfeeding.

These are not all the possible side effects of BUTALBITAL, ASPIRIN, CAFFEINE and CODEINE PHOSPHATE. Call your healthcare provider for medical advice about side effects. You may report side effects to FDA at 1-800-FDA-1088. For more information go to dailymed.nlm.nih.gov

Manufactured by: Jerome Stevens Pharmaceuticals, Inc. Bohemia, NY 11716
Distributed by: Amneal Pharmaceuticals LLC, Bridgewater, NJ 08807

This Medication Guide has been approved by the U.S. Food and Drug Administration.

Issued: 11/2025

PRINCIPAL DISPLAY PANEL

NDC 69238-1993-1

BUTALBITAL, ASPIRIN, CAFFEINE AND CODEINE PHOSPHATE CAPSULES USP, 50 mg/325 mg/40 mg/30 mg CIII

Rx ONLY

100 CAPSULES